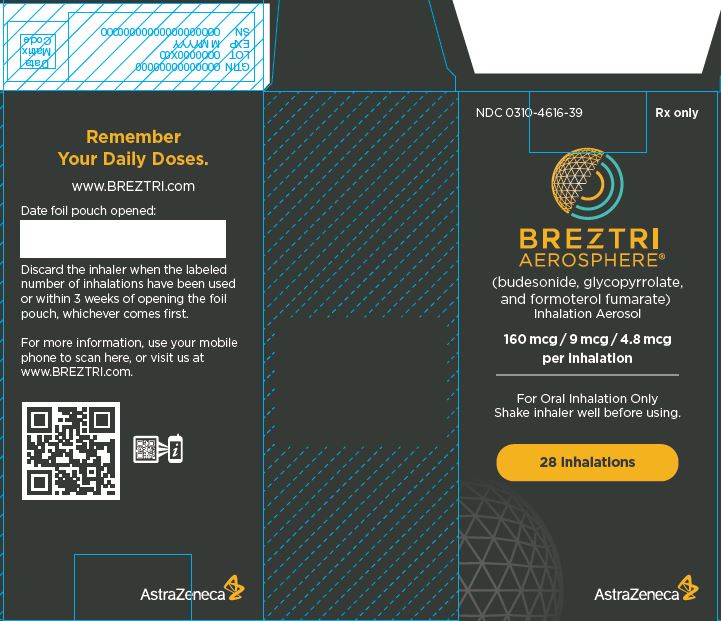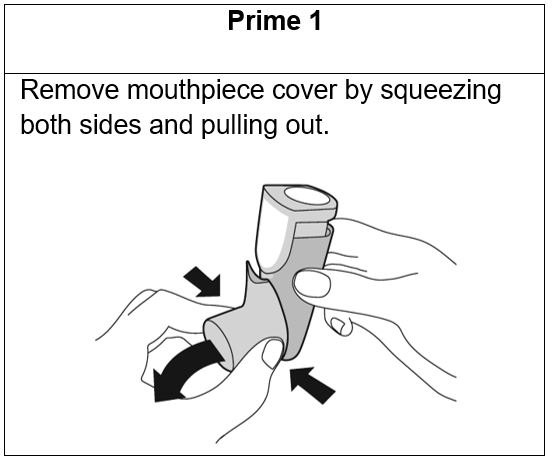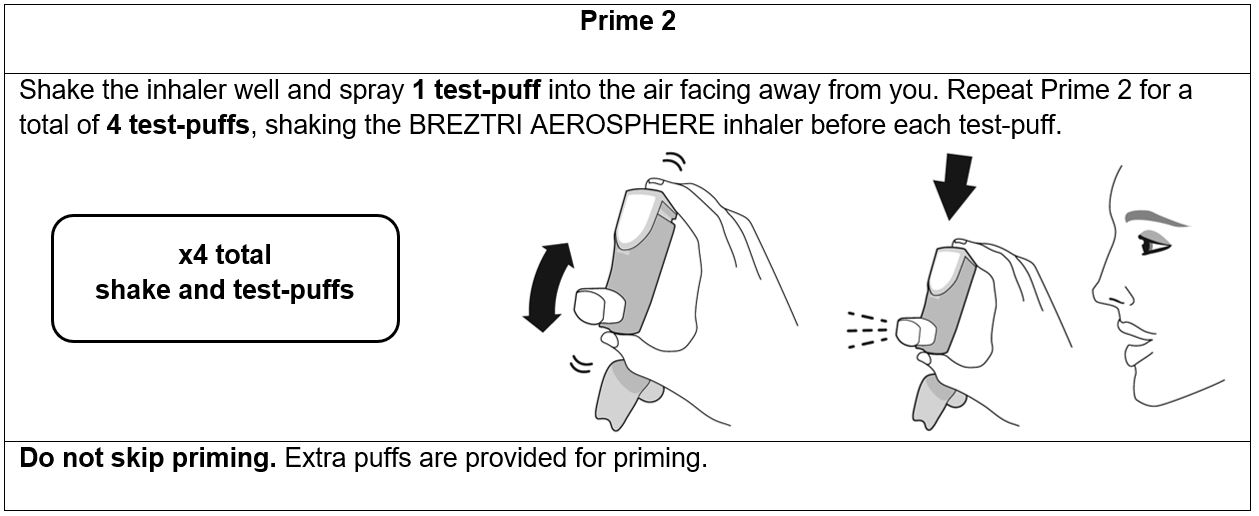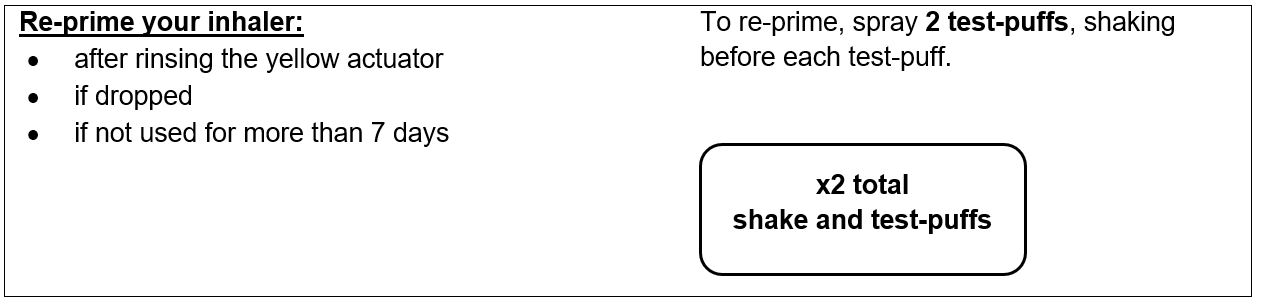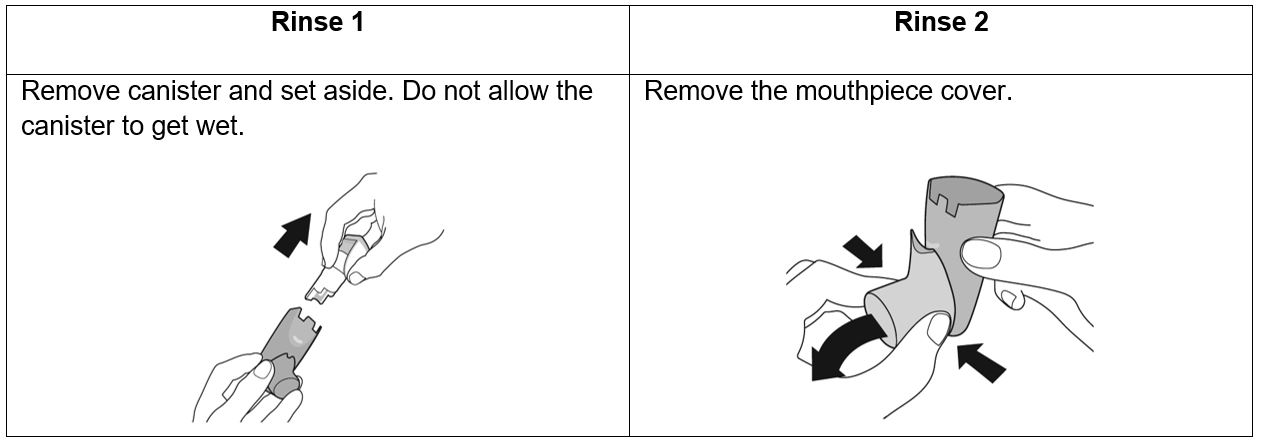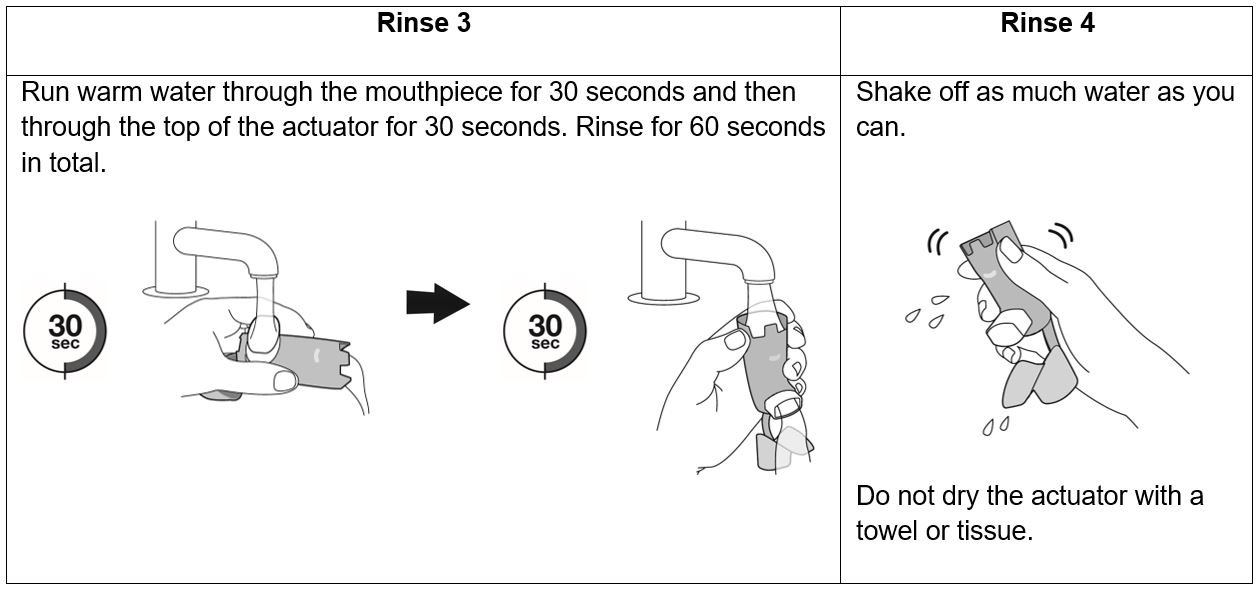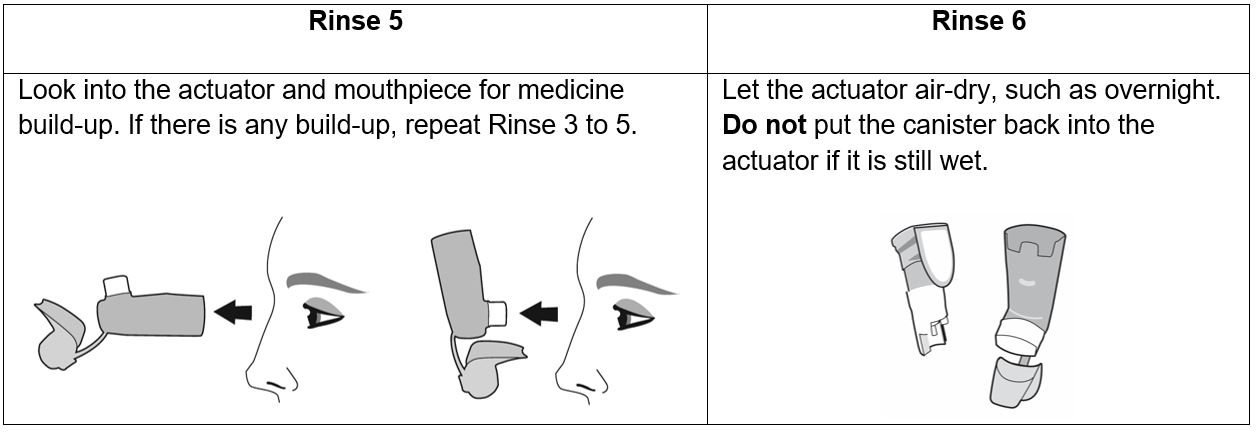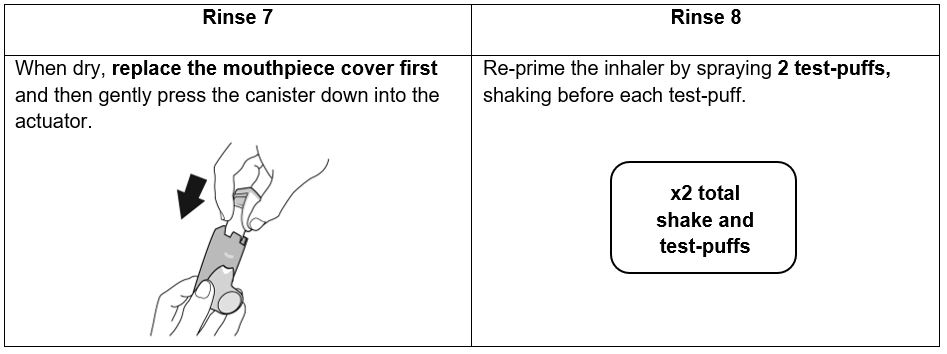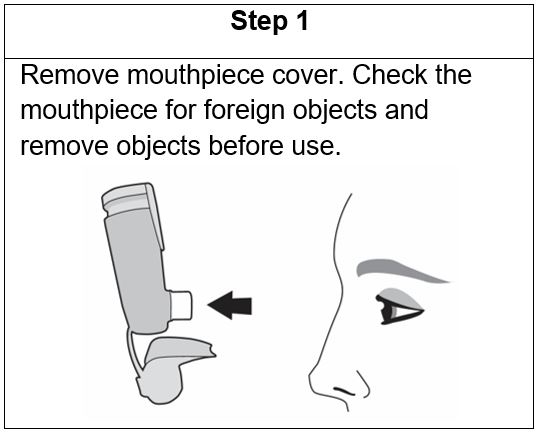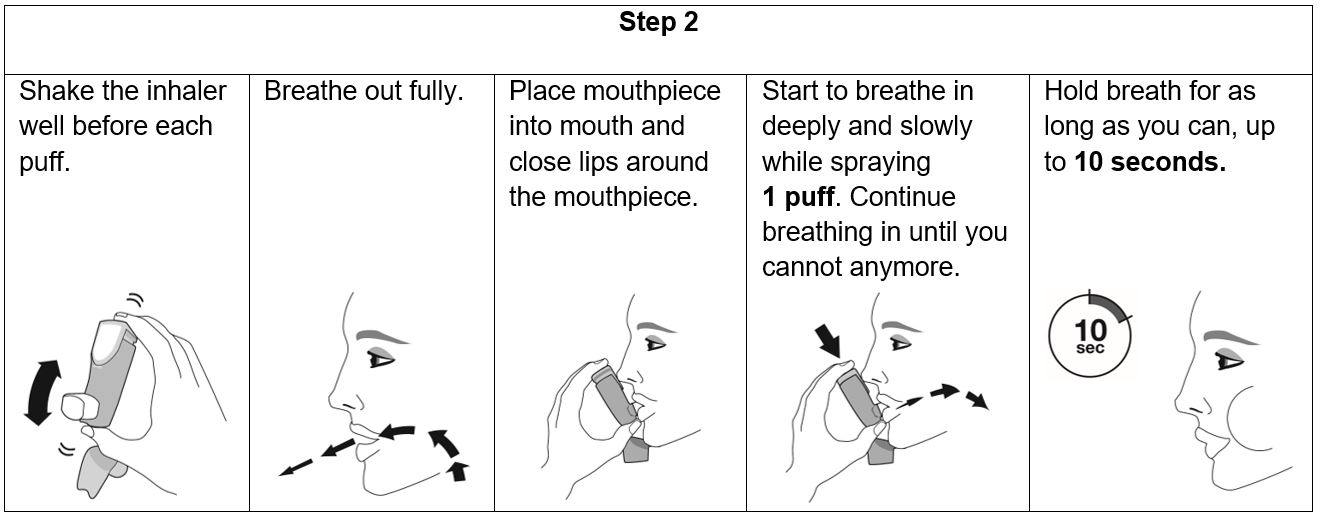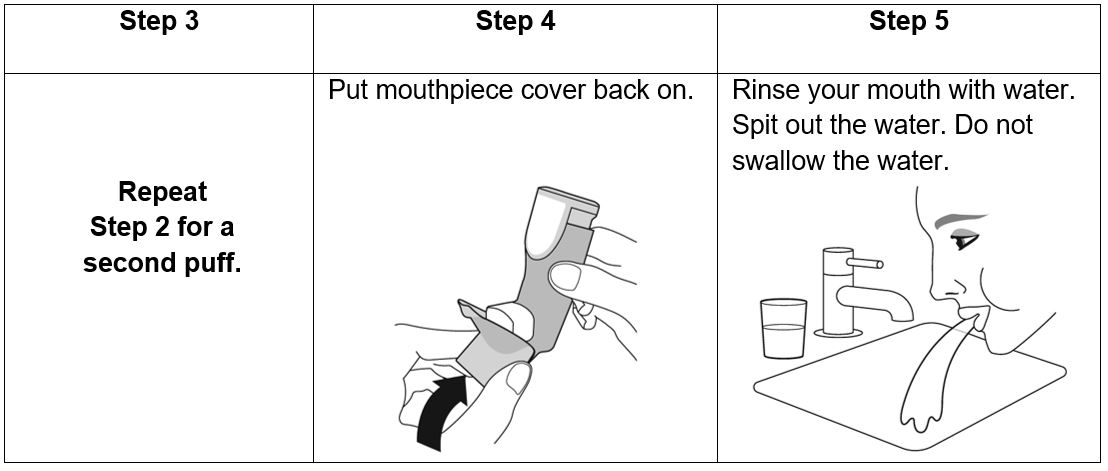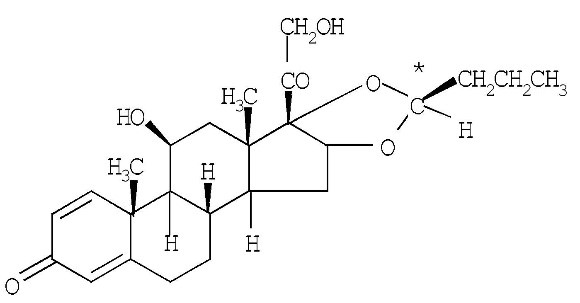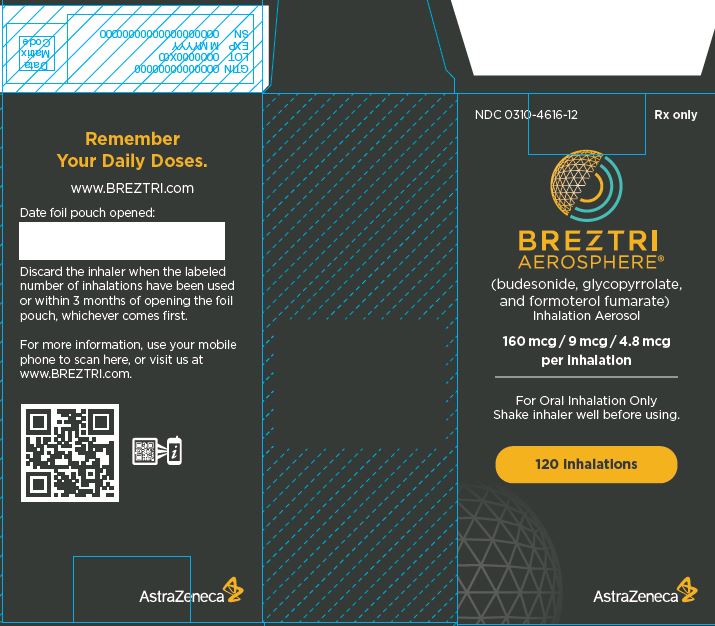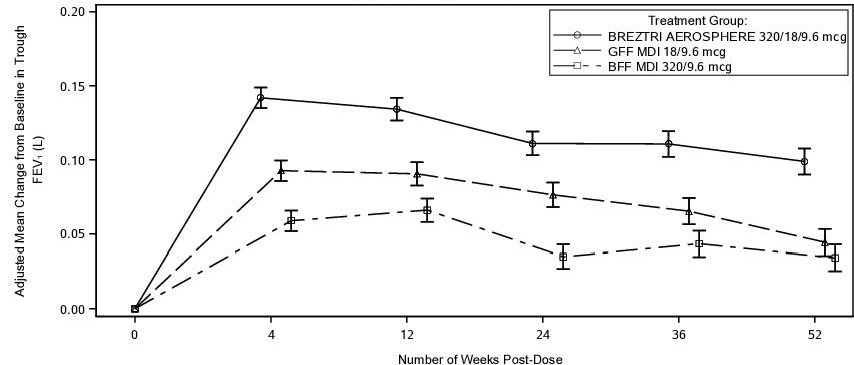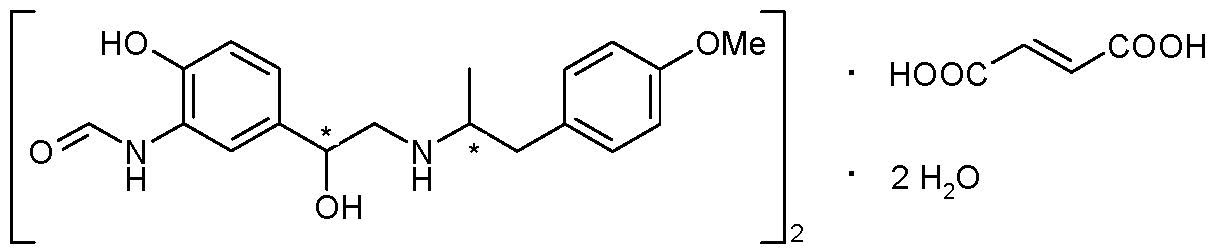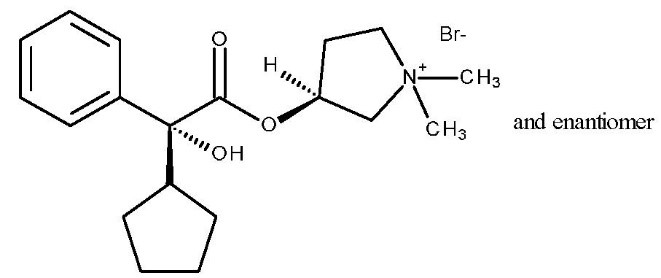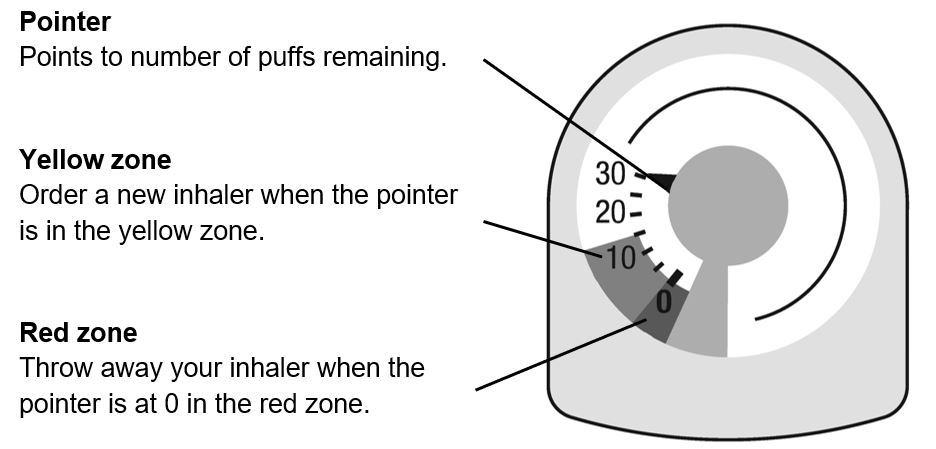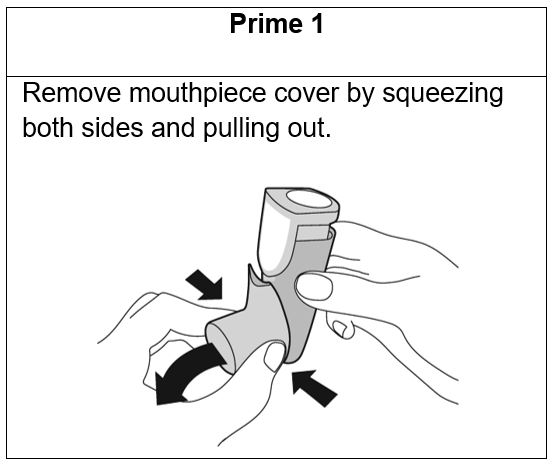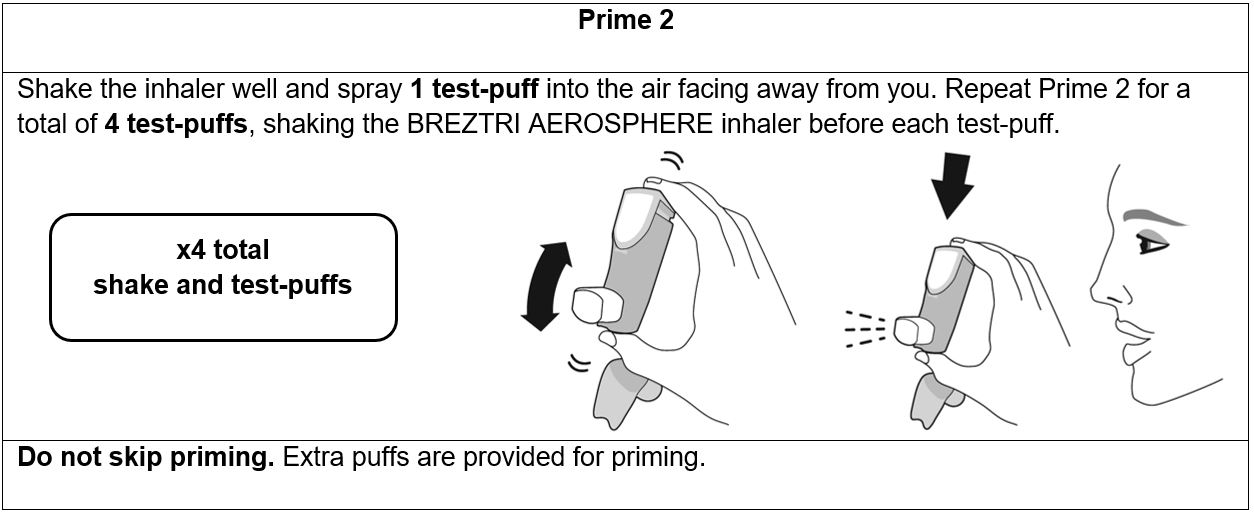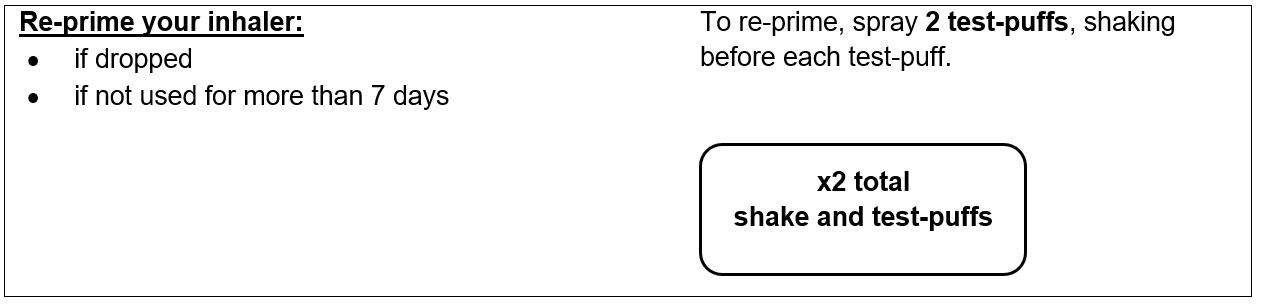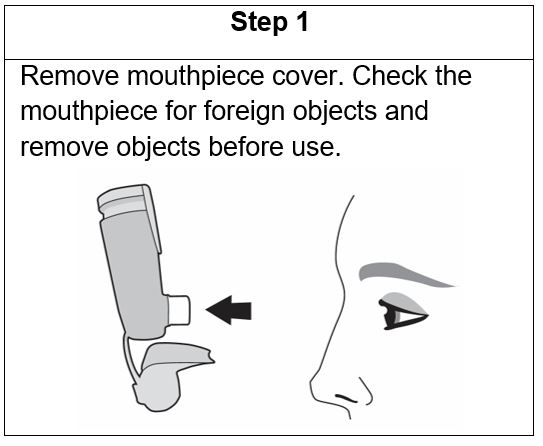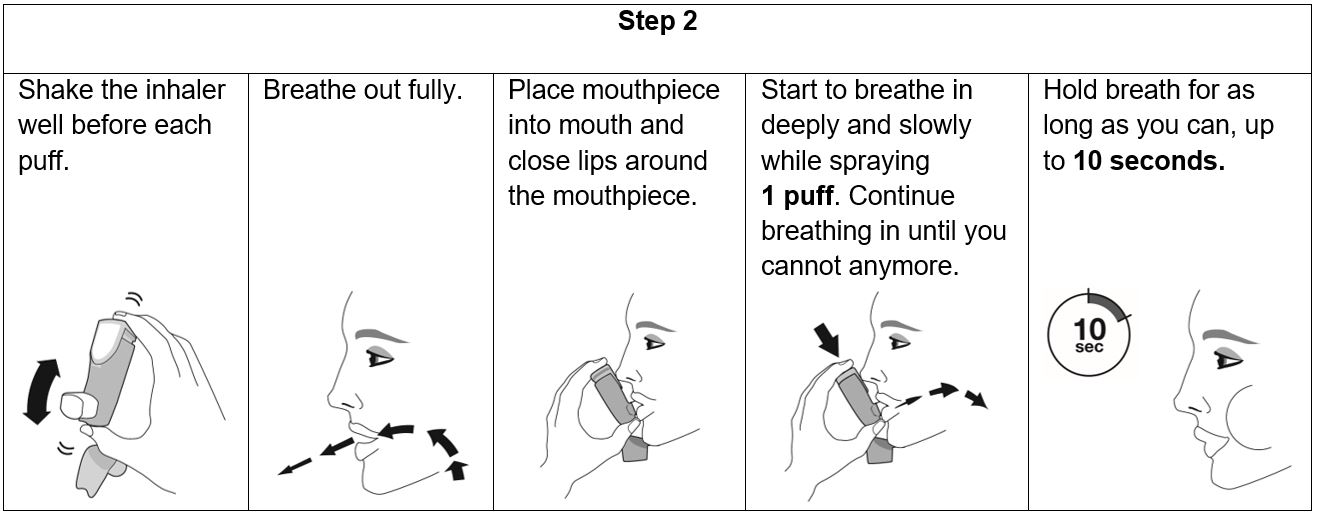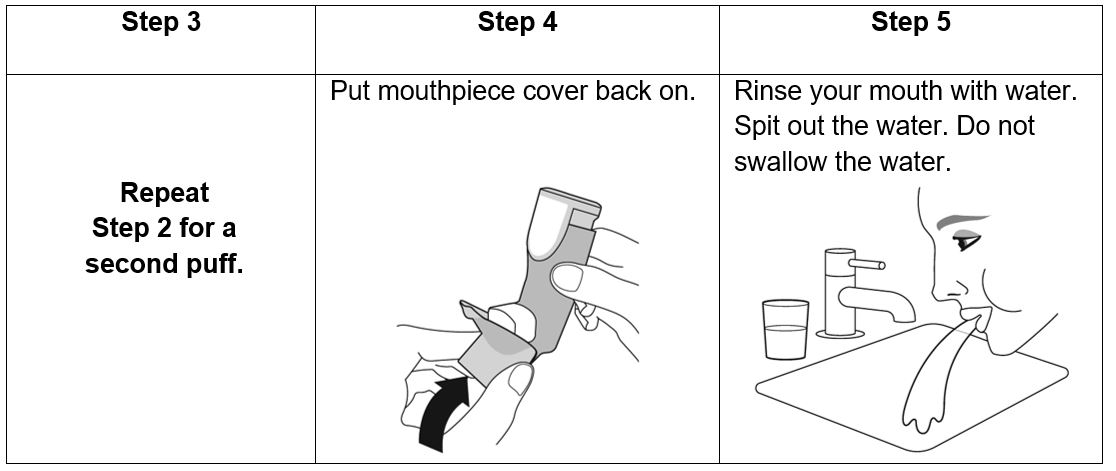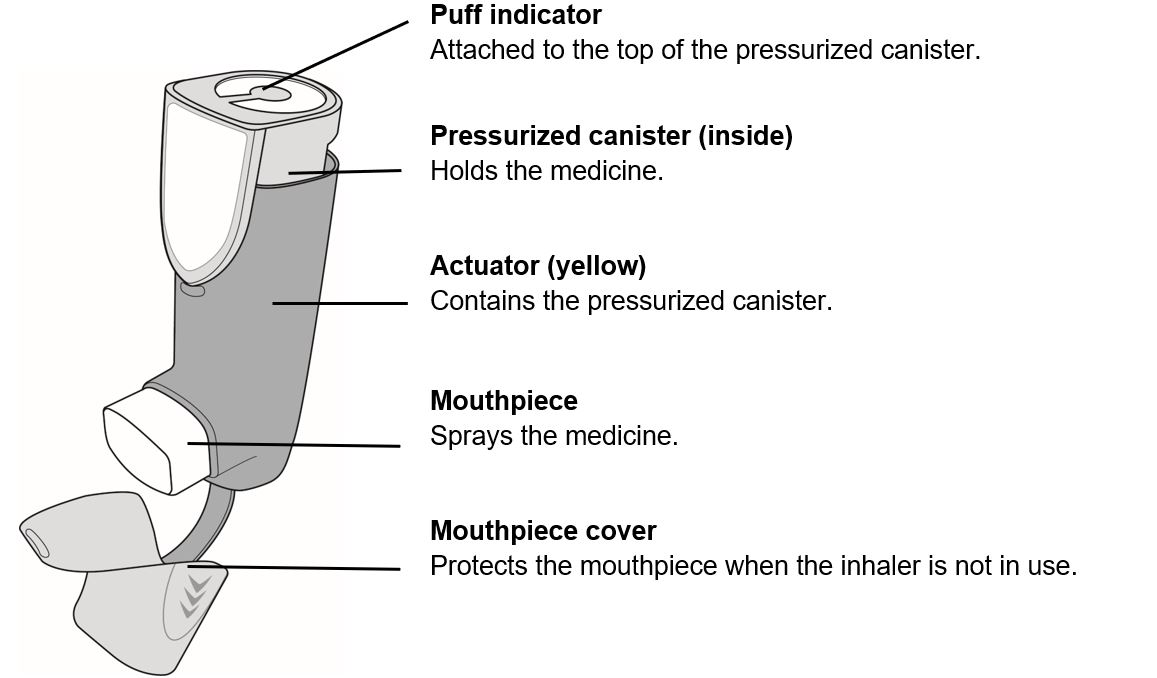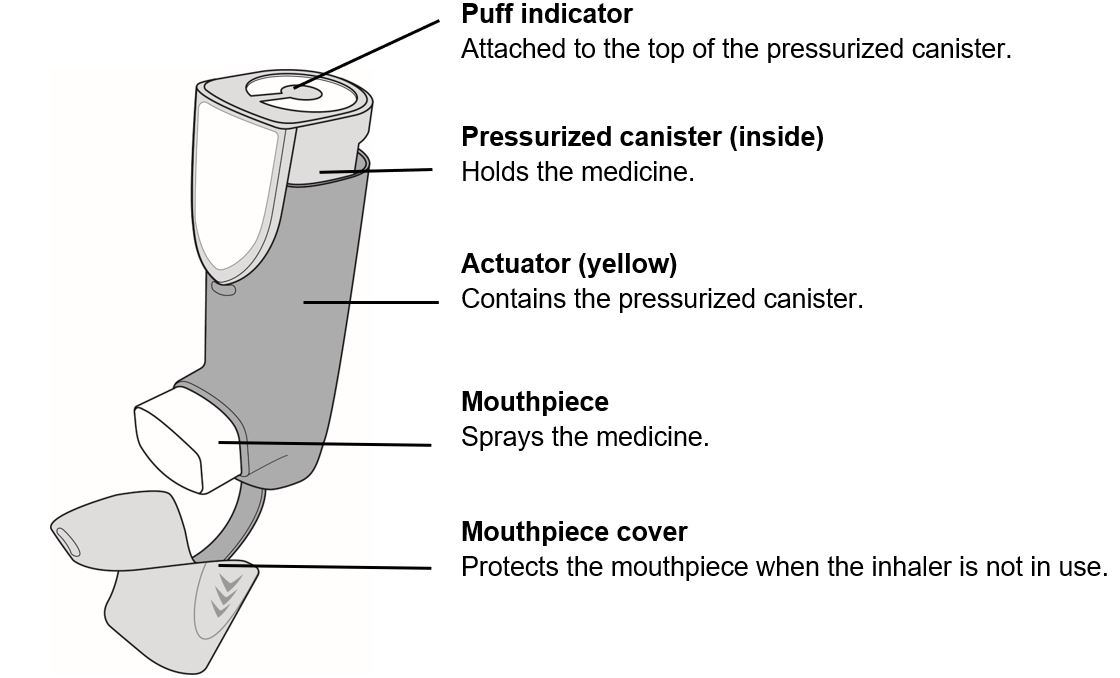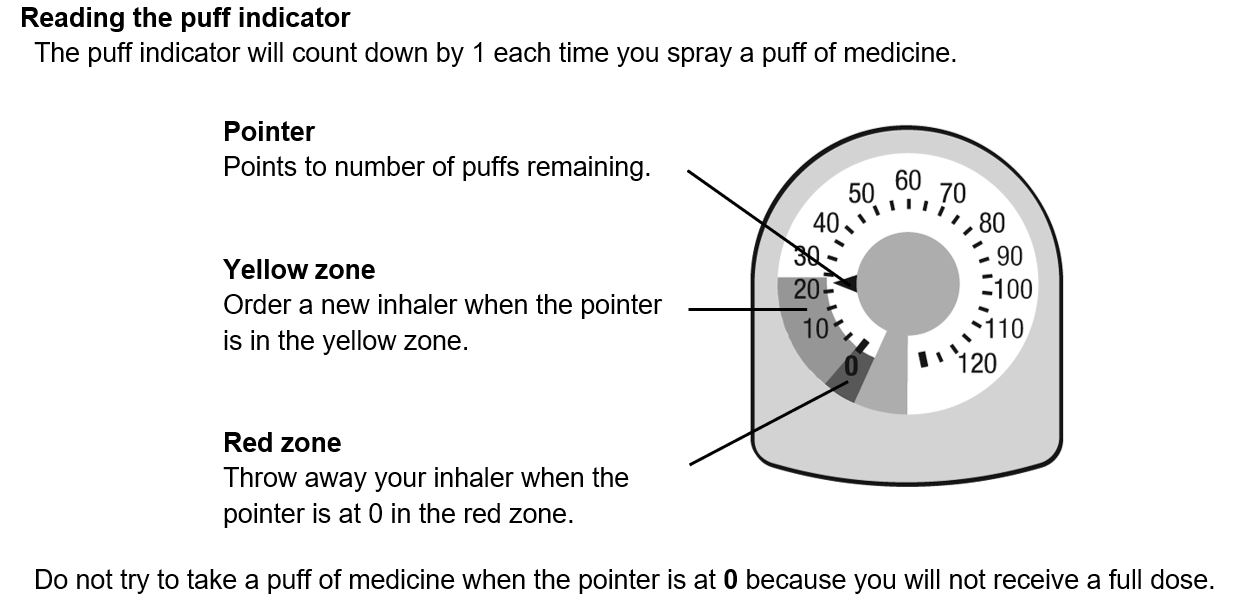 DRUG LABEL: BREZTRI
NDC: 0310-4616 | Form: AEROSOL, METERED
Manufacturer: AstraZeneca Pharmaceuticals LP
Category: prescription | Type: HUMAN PRESCRIPTION DRUG LABEL
Date: 20220126

ACTIVE INGREDIENTS: BUDESONIDE 160 ug/1 1; GLYCOPYRROLATE 9 ug/1 1; FORMOTEROL 4.8 ug/1 1
INACTIVE INGREDIENTS: 1,2-DISTEAROYL-SN-GLYCERO-3-PHOSPHOCHOLINE; CALCIUM CHLORIDE; NORFLURANE

HIGHLIGHTS OF PRESCRIBING INFORMATION

These highlights do not include all the information needed to use BREZTRI AEROSPHERE safely and effectively. See full prescribing information for BREZTRI AEROSPHERE.
BREZTRI AEROSPHERE® (budesonide, glycopyrrolate, and formoterol fumarate) inhalation aerosol, for oral inhalation use
Initial U.S. Approval: 2020

1 INDICATIONS AND USAGE

BREZTRI AEROSPHERE is a combination of budesonide, an inhaled corticosteroid (ICS); glycopyrrolate, an anticholinergic; and formoterol fumarate, a long-acting beta2-adrenergic agonist (LABA), indicated for the maintenance treatment of patients with chronic obstructive pulmonary disease (COPD). (1)

Limitations of Use: Not indicated for the relief of acute bronchospasm or for the treatment of asthma. (1, 5.1, 5.2)

2 DOSAGE AND ADMINISTRATION

- For oral inhalation only. (2)
- Maintenance treatment of COPD: 2 inhalations of BREZTRI AEROSPHERE twice daily administered by oral inhalation. (2)

3 DOSAGE FORMS AND STRENGTHS

- Inhalation aerosol: Pressurized metered dose inhaler containing a combination of budesonide (160 mcg), glycopyrrolate (9 mcg), and formoterol fumarate (4.8 mcg) per inhalation. (3)

4 CONTRAINDICATIONS

Hypersensitivity to budesonide, glycopyrrolate, formoterol fumarate, or to any of the excipients. (4)

5 WARNINGS AND PRECAUTIONS

- LABA as monotherapy (without an inhaled-corticosteroid) is associated with an increased risk of serious asthma-related events. (5.1)
- Do not initiate in acutely deteriorating COPD. Do not use to relieve acute symptoms. (5.2)
- Do not use in combination with an additional therapy containing a LABA because of the risk of overdose. (5.3)
- Candida albicans infection of the mouth and pharynx may occur. Monitor patients periodically. Advise the patient to rinse his/her mouth with water without swallowing after inhalation to help reduce the risk. (5.4)
- Increased risk of pneumonia in patients with COPD. Monitor patients for signs and symptoms of pneumonia. (5.5)
- Potential worsening of infections (e.g., existing tuberculosis; fungal, bacterial, viral, or parasitic infections; ocular herpes simplex). Use with caution in patients with these infections. More serious or even fatal course of chickenpox or measles can occur in susceptible patients. (5.6)
- Risk of impaired adrenal function when transferring from systemic corticosteroids. Taper patients slowly from systemic corticosteroids if transferring to BREZTRI AEROSPHERE. (5.7)
- Hypercorticism and adrenal suppression may occur with very high dosages or at the regular dosage in susceptible individuals. If such changes occur, consider appropriate therapy. (5.8)
- If paradoxical bronchospasm occurs, discontinue BREZTRI AEROSPHERE and institute alternative therapy. (5.10)
- Use with caution in patients with cardiovascular disorders because of beta-adrenergic stimulation. (5.12)
- Assess for decrease in bone mineral density initially and periodically thereafter. (5.13)
- Glaucoma and cataracts may occur with long-term use of ICS. Worsening of narrow-angle glaucoma may occur. Use with caution in patients with narrow-angle glaucoma and instruct patients to contact a healthcare provider immediately if symptoms occur. Consider referral to an ophthalmologist in patients who develop ocular symptoms or use BREZTRI AEROSPHERE long term. (5.14)
- Worsening of urinary retention may occur. Use with caution in patients with prostatic hyperplasia or bladder-neck obstruction and instruct patients to contact a healthcare provider immediately if symptoms occur. (5.15)
- Use with caution in patients with convulsive disorders, thyrotoxicosis, diabetes mellitus, and ketoacidosis. (5.16)
- Be alert to hypokalemia and hyperglycemia. (5.17)

6 ADVERSE REACTIONS

Most common adverse reactions (incidence ≥ 2%) are upper respiratory tract infection, pneumonia, back pain, oral candidiasis, influenza, muscle spasm, urinary tract infection, cough, sinusitis and diarrhea. (6.1)

To report SUSPECTED ADVERSE REACTIONS, contact AstraZeneca at 1-800-236-9933 or FDA at 1-800-FDA-1088 or www.fda.gov/medwatch.

7 DRUG INTERACTIONS

- Strong cytochrome P450 3A4 inhibitors (e.g. ritonavir): Use with caution. May cause systemic corticosteroid effects. (7.1)
- Other adrenergic drugs may potentiate effect: Use with caution. (7.2)
- Diuretics, xanthine derivatives or steroids may potentiate hypokalemia or ECG changes. Use with caution. (7.3, 7.4)
- Monoamine oxidase inhibitors and tricyclic antidepressants: Use with extreme caution. May potentiate effect of formoterol fumarate on cardiovascular system. (7.5)
- Beta-blockers: Use with caution. May block bronchodilatory effects of beta-agonists and produce severe bronchospasm. (7.6)
- Anticholinergics: May interact additively with concomitantly used anticholinergic medications. Avoid administration of BREZTRI AEROSPHERE with other anticholinergic-containing drugs. (7.7)

8 USE IN SPECIFIC POPULATIONS

Hepatic impairment: Budesonide and formoterol fumarate systemic exposure may increase in patients with severe hepatic impairment. Monitor patients for signs of increased drug exposure. (8.6, 12.3)

Renal impairment: In patients with severe renal impairment, use should be considered only if the potential benefit of the treatment outweighs the risk (8.7).

FULL PRESCRIBING INFORMATION

1 INDICATIONS AND USAGE

BREZTRI AEROSPHERE is indicated for the maintenance treatment of patients with chronic obstructive pulmonary disease (COPD).

Limitations of Use:

BREZTRI AEROSPHERE is not indicated for the relief of acute bronchospasm or for the treatment of asthma [see Warnings and Precautions (5.1, 5.2)].

2 DOSAGE AND ADMINISTRATION

2.1 Recommended Dosage and Administration

The recommended dosage of BREZTRI AEROSPHERE is budesonide 320 mcg, glycopyrrolate 18 mcg and formoterol fumarate 9.6 mcg (administered as 2 inhalations of BREZTRI AEROSPHERE [budesonide/glycopyrrolate/formoterol fumarate 160 mcg/9 mcg/4.8 mcg]) twice daily, in the morning and in the evening, by oral inhalation. Do not take more than two inhalations twice daily.

After inhalation, rinse mouth with water without swallowing.

2.2 Preparation

Prime BREZTRI AEROSPHERE before using for the first time. Priming BREZTRI AEROSPHERE is essential to ensure appropriate drug content in each actuation. Prime BREZTRI AEROSPHERE by releasing 4 sprays into the air away from the face, shaking well before each spray.

If the inhaler has not been used for more than 7 days, is dropped, or after weekly rinsing, prime the inhaler again by releasing 2 sprays into the air away from the face, shaking well before each spray.

2.3 Dose counter

BREZTRI AEROSPHERE canister has an attached dose indicator (also known as puff indicator), which indicates how many inhalations (puffs) remain. The dose indicator display has a pointer which will move after every actuation. When nearing the end of the usable inhalations, the pointer is in the yellow zone. BREZTRI AEROSPHERE should be discarded when the pointer is at zero which is in the red zone.

3 DOSAGE FORMS AND STRENGTHS

Inhalation aerosol: a pressurized metered dose inhaler that delivers a combination of 160 mcg budesonide, 9 mcg glycopyrrolate, and 4.8 mcg formoterol fumarate per inhalation.

4 CONTRAINDICATIONS

BREZTRI AEROSPHERE is contraindicated in patients who have demonstrated hypersensitivity to budesonide, glycopyrrolate, formoterol, or any of the excipients [see Warnings and Precautions (5.11) and Description (11)].

5 WARNINGS AND PRECAUTIONS

5.1 Serious Asthma-Related Events – Hospitalizations, Intubations, Death

The safety and efficacy of BREZTRI AEROSPHERE in patients with asthma have not been established. BREZTRI AEROSPHERE is not indicated for the treatment of asthma.

Use of long-acting beta2-adrenergic agonists (LABA) as monotherapy [without inhaled corticosteroid (ICS)] for asthma is associated with an increased risk of asthma-related death. Available data from controlled clinical trials also suggest that use of LABA as monotherapy increases the risk of asthma-related hospitalization in pediatric and adolescent patients. These findings are considered a class effect of LABA monotherapy. When a LABA is used in fixed-dose combination with ICS, data from large clinical trials do not show a significant increase in the risk of serious asthma-related events (hospitalizations, intubations, death) compared with ICS alone.

Available data do not suggest an increased risk of death with use of LABA in patients with COPD.

5.2 Deterioration of Disease and Acute Episodes

BREZTRI AEROSPHERE should not be initiated in patients with acutely deteriorating COPD, which may be a life-threatening condition. BREZTRI AEROSPHERE has not been studied in patients with acutely deteriorating COPD. The use of BREZTRI AEROSPHERE in this setting is not appropriate.

BREZTRI AEROSPHERE should not be used for the relief of acute symptoms, i.e., as rescue therapy for the treatment of acute episodes of bronchospasm. BREZTRI AEROSPHERE has not been studied in the relief of acute symptoms and extra doses should not be used for that purpose. Acute symptoms should be treated with an inhaled short-acting beta2-agonist.

When beginning treatment with BREZTRI AEROSPHERE, patients who have been taking inhaled, short-acting beta2-agonists on a regular basis (e.g., four times a day) should be instructed to discontinue the regular use of these drugs and use them only for symptomatic relief of acute respiratory symptoms. When prescribing BREZTRI AEROSPHERE, the healthcare provider should also prescribe an inhaled, short acting beta2-agonist and instruct the patient on how it should be used. Increasing inhaled beta2-agonist use is a signal of deteriorating disease for which prompt medical attention is indicated.

COPD may deteriorate acutely over a period of hours or chronically over several days or longer. If BREZTRI AEROSPHERE no longer controls symptoms, or the patient’s inhaled, short-acting beta2-agonist becomes less effective or the patient needs more inhalations of short-acting beta2-agonist than usual, these may be markers of deterioration of disease. In this setting, re-evaluate the patient and the COPD treatment regimen at once. The daily dosage of BREZTRI AEROSPHERE should not be increased beyond the recommended dose.

5.3 Avoid Excessive Use of BREZTRI AEROSPHERE and Avoid Use with other Long-Acting Beta2-Agonists

As with other inhaled drugs containing beta2-adrenergic agents, BREZTRI AEROSPHERE should not be used more often than recommended, at higher doses than recommended, or in conjunction with other medications containing LABA, as an overdose may result. Clinically significant cardiovascular effects and fatalities have been reported in association with excessive use of inhaled sympathomimetic drugs. Patients using BREZTRI AEROSPHERE should not use another medicine containing a LABA (e.g., salmeterol, formoterol fumarate, arformoterol tartrate, indacaterol) for any reason [see Drug Interactions (7.1)].

5.4 Oropharyngeal Candidiasis

BREZTRI AEROSPHERE contains budesonide, an ICS. Localized infections of the mouth and pharynx with Candida albicans have occurred in subjects treated with orally inhaled drug products containing budesonide. When such an infection develops, it should be treated with appropriate local or systemic (i.e., oral) antifungal therapy while treatment with BREZTRI AEROSPHERE continues. In some cases, therapy with BREZTRI AEROSPHERE may need to be interrupted. Advise the patient to rinse his/her mouth with water without swallowing following administration of BREZTRI AEROSPHERE to help reduce the risk of oropharyngeal candidiasis.

5.5 Pneumonia

Lower respiratory tract infections, including pneumonia, have been reported following the inhaled administration of corticosteroids. Physicians should remain vigilant for the possible development of pneumonia in patients with COPD as the clinical features of pneumonia and exacerbations frequently overlap.

In a 52-week trial of subjects with COPD (n = 8,529), the incidence of confirmed pneumonia was 4.2% for BREZTRI AEROSPHERE 320 mcg/18 mcg/9.6 mcg (n = 2144), 3.5% for budesonide, glycopyrrolate and formoterol fumarate [BGF MDI 160 mcg/18 mcg/9.6 mcg] (n = 2124), 2.3% for GFF MDI 18 mcg/9.6 mcg (n = 2125) and 4.5% for BFF MDI 320 mcg/9.6 mcg (n = 2136).

Fatal cases of pneumonia occurred in 2 subjects receiving BGF MDI 160 mcg/18 mcg/9.6 mcg, 3 subjects receiving GFF MDI 18 mcg/9.6 mcg, and no subjects receiving BREZTRI AEROSPHERE 320 mcg/18 mcg/9.6 mcg.

In a 24-week trial of subjects with COPD (n = 1,896), the incidence of confirmed pneumonia was 1.9% for BREZTRI AEROSPHERE 320 mcg/18 mcg/9.6 mcg (n = 639), 1.6% for glycopyrrolate and formoterol fumarate [GFF MDI 18 mcg/9.6 mcg] (n = 625) and 1.9% for budesonide and formoterol fumarate [BFF MDI 320 mcg/9.6 mcg] (n = 320). There were no fatal cases of pneumonia in the study.

5.6 Immunosuppression and Risk of Infections

Patients who are using drugs that suppress the immune system are more susceptible to infection than healthy individuals. Chicken pox and measles, for example, can have a more serious or even fatal course in susceptible children or adults using corticosteroids. In such children or adults who have not had these diseases or been properly immunized, particular care should be taken to avoid exposure. How the dose, route, and duration of corticosteroid administration affects the risk of developing a disseminated infection is not known. The contribution of the underlying disease and/or prior corticosteroid treatment to the risk is also not known. If a patient is exposed to chickenpox, prophylaxis with varicella zoster immune globulin (VZIG) may be indicated. If exposed to measles, prophylaxis with pooled intramuscular immunoglobulin (IG) may be indicated (see the Prescribing Information for VZIG and IG). If chicken pox develops, treatment with antiviral agents may be considered.

ICS should be used with caution, if at all, in patients with active or quiescent tuberculosis infections of the respiratory tract; untreated systemic fungal, bacterial, viral, or parasitic infections; or ocular herpes simplex.

5.7 Transferring Patients from Systemic Corticosteroid Therapy

HPA Suppression/Adrenal Insufficiency

Particular care is needed for patients who have been transferred from systemically active corticosteroids to ICS because deaths due to adrenal insufficiency have occurred in patients during and after transfer from systemic corticosteroids to less systemically available ICS. After withdrawal from systemic corticosteroids, a number of months are required for recovery of hypothalamic-pituitary-adrenal (HPA) function.

Patients who have been previously maintained on 20 mg or more per day of prednisone (or its equivalent) may be most susceptible, particularly when their systemic corticosteroids have been almost completely withdrawn. During this period of HPA suppression, patients may exhibit signs and symptoms of adrenal insufficiency when exposed to trauma, surgery, or infection (particularly gastroenteritis) or other conditions associated with severe electrolyte loss. Although BREZTRI AEROSPHERE may provide control of COPD symptoms during these episodes, in recommended doses it supplies less than normal physiological amounts of glucocorticoid systemically and does not provide the mineralocorticoid activity that is necessary for coping with these emergencies.

During periods of stress, or a severe COPD exacerbation, patients who have been withdrawn from systemic corticosteroids should be instructed to resume oral corticosteroids (in large doses) immediately and to contact their healthcare practitioner for further instruction. These patients should also be instructed to carry a warning card indicating that they may need supplementary systemic corticosteroids during periods of stress, or a severe COPD exacerbation.

Patients requiring oral corticosteroids should be weaned slowly from systemic corticosteroid use after transferring to BREZTRI AEROSPHERE. Prednisone reduction can be accomplished by reducing the daily prednisone dose by 2.5 mg on a weekly basis during therapy with BREZTRI AEROSPHERE. Lung function (forced expiratory volume in 1 second [FEV1] or morning peak expiratory flow [PEF]), beta-agonist use, and COPD symptoms should be carefully monitored during withdrawal of oral corticosteroids. In addition, patients should be observed for signs and symptoms of adrenal insufficiency, such as fatigue, lassitude, weakness, nausea and vomiting, and hypotension.

Unmasking of Allergic Conditions Previously Suppressed by Systemic Corticosteroids

Transfer of patients from systemic corticosteroid therapy to BREZTRI AEROSPHERE may unmask allergic conditions previously suppressed by the systemic corticosteroid therapy (e.g., rhinitis, conjunctivitis, eczema, arthritis, eosinophilic conditions).

Corticosteroid Withdrawal Symptoms

During withdrawal from oral corticosteroids, some patients may experience symptoms of systemically active corticosteroid withdrawal (e.g., joint and/or muscular pain, lassitude, depression) despite maintenance or even improvement of respiratory function.

5.8 Hypercorticism and Adrenal Suppression

Inhaled budesonide is absorbed into the circulation and can be systemically active. Effects of budesonide on the HPA axis are not observed with the therapeutic doses of budesonide in BREZTRI AEROSPHERE. However, exceeding the recommended dosage or coadministration with a strong cytochrome P450 3A4 (CYP3A4) inhibitor may result in HPA dysfunction [see Warnings and Precautions (5.9) and Drug Interactions (7.1)].

Because of the possibility of significant systemic absorption of ICS, patients treated with BREZTRI AEROSPHERE should be observed carefully for any evidence of systemic corticosteroid effects. Particular care should be taken in observing patients postoperatively or during periods of stress for evidence of inadequate adrenal response.

It is possible that systemic corticosteroid effects, such as hypercorticism and adrenal suppression (including adrenal crisis) may appear in a small number of patients who are sensitive to these effects. If such effects occur, appropriate therapy should be initiated as needed.

5.9 Drug Interactions with Strong Cytochrome P450 3A4 Inhibitors

Caution should be exercised when considering the coadministration of BREZTRI AEROSPHERE with long-term ketoconazole, and other known strong CYP3A4 inhibitors (e.g., ritonavir, atazanavir, clarithromycin, indinavir, itraconazole, nefazodone, nelfinavir, saquinavir, telithromycin) because adverse effects related to increased systemic exposure to budesonide may occur [see Drug Interactions (7.1) and Clinical Pharmacology (12.3)].

5.10 Paradoxical Bronchospasm

As with other inhaled therapies, BREZTRI AEROSPHERE can produce paradoxical bronchospasm, which may be life-threatening. If paradoxical bronchospasm occurs following dosing with BREZTRI AEROSPHERE, it should be treated immediately with an inhaled, short-acting bronchodilator; BREZTRI AEROSPHERE should be discontinued immediately and alternative therapy should be instituted.

5.11 Hypersensitivity Reactions including Anaphylaxis

Immediate hypersensitivity reactions have been reported after administration of budesonide, glycopyrrolate or formoterol fumarate, the components of BREZTRI AEROSPHERE. If signs suggesting allergic reactions occur, in particular, angioedema (including difficulties in breathing or swallowing, swelling of tongue, lips, and face), urticaria, or skin rash, BREZTRI AEROSPHERE should be stopped at once and alternative treatment should be considered [see Contraindications (4)].

5.12 Cardiovascular Effects

Formoterol fumarate, like other beta2-agonists, can produce a clinically significant cardiovascular effect in some patients as measured by increases in pulse rate, systolic or diastolic blood pressure, and also cardiac arrhythmias, such as supraventricular tachycardia and extrasystoles [see Clinical Pharmacology (12.2)].

If such effects occur, BREZTRI AEROSPHERE may need to be discontinued. In addition, beta-agonists have been reported to produce electrocardiographic changes, such as flattening of the T wave, prolongation of the QTc interval, and ST segment depression, although the clinical significance of these findings is unknown. Therefore, BREZTRI AEROSPHERE should be used with caution in patients with cardiovascular disorders, especially coronary insufficiency, cardiac arrhythmias, and hypertension.

5.13 Reduction in Bone Mineral Density

Decreases in bone mineral density (BMD) have been observed with long-term administration of products containing ICS. The clinical significance of small changes in BMD with regard to long-term consequences such as fracture is unknown. Patients with major risk factors for decreased bone mineral content, such as prolonged immobilization, family history of osteoporosis, postmenopausal status, tobacco use, advanced age, poor nutrition, or chronic use of drugs that can reduce bone mass (e.g., anticonvulsants, oral corticosteroids) should be monitored and treated with established standards of care. Since patients with COPD often have multiple risk factors for reduced BMD, assessment of BMD is recommended prior to initiating BREZTRI AEROSPHERE and periodically thereafter. If significant reductions in BMD are seen and BREZTRI AEROSPHERE is still considered medically important for that patient's COPD therapy, use of therapy to treat or prevent osteoporosis should be strongly considered.

In a subset of COPD patients in a 24-week trial with a 28-week safety extension that evaluated BREZTRI AEROSPHERE 320/18/9.6 mcg and GFF MDI 18/9.6 mcg, the effects on BMD endpoints were evaluated. BMD evaluations were performed at baseline and 52-weeks using dual energy x-ray absorptiometry (DEXA) scans. Mean percent changes in BMD from baseline was -0.1% for BREZTRI AEROSPHERE 320/18/9.6 mcg and 0.4% for GFF MDI 18/9.6 mcg [see Clinical Studies (14)].

5.14 Glaucoma and Cataracts, Worsening of Narrow-Angle Glaucoma

Glaucoma, increased intraocular pressure, and cataracts have been reported in patients with COPD following the long-term administration of ICS or with use of inhaled anticholinergics. BREZTRI AEROSPHERE should be used with caution in patients with narrow-angle glaucoma. Prescribers and patients should be alert for signs and symptoms of acute narrow-angle glaucoma (e.g., eye pain or discomfort, blurred vision, visual halos or colored images in association with red eyes from conjunctival congestion and corneal edema). Instruct patients to consult a physician immediately should any of these signs or symptoms develop. Consider referral to an ophthalmologist in patients who develop ocular symptoms or use BREZTRI AEROSPHERE long term.

In a 52-week trial that evaluated BREZTRI AEROSPHERE 320/18/9.6 mcg, GFF MDI 18/9.6 mcg, and BFF MDI 320/9.6 mcg in subjects with COPD, the incidence of cataracts ranged from 0.7% to 1.0% across groups.

5.15 Worsening of Urinary Retention

BREZTRI AEROSPHERE, like all therapies containing an anticholinergic, should be used with caution in patients with urinary retention. Prescribers and patients should be alert for signs and symptoms of prostatic hyperplasia or bladder-neck obstruction (e.g., difficulty passing urine, painful urination), especially in patients with prostatic hyperplasia or bladder neck obstruction. Instruct patients to consult a physician immediately should any of these signs or symptoms develop.

5.16 Coexisting Conditions

BREZTRI AEROSPHERE, like all therapies containing sympathomimetic amines, should be used with caution in patients with convulsive disorders or thyrotoxicosis and in those who are unusually responsive to sympathomimetic amines. Doses of the related beta2-adrenoceptor agonist albuterol, when administered intravenously, have been reported to aggravate preexisting diabetes mellitus and ketoacidosis.

5.17 Hypokalemia and Hyperglycemia

Beta-adrenergic agonists may produce significant hypokalemia in some patients, possibly through intracellular shunting, which has the potential to produce adverse cardiovascular effects. The decrease in serum potassium is usually transient, not requiring supplementation. Beta2-agonist therapies may produce transient hyperglycemia in some patients.

6 ADVERSE REACTIONS

The following adverse reactions are discussed in greater detail in other sections of the labeling.

- Serious asthma-related events – hospitalizations, intubations, death [see Warnings and Precautions (5.1)]
- Oropharyngeal candidiasis infection [see Warnings and Precautions (5.4)]
- Increased risk of pneumonia in COPD [see Warnings and Precautions (5.5)]
- Immunosuppression and risk of infections [see Warnings and Precautions (5.6)]
- Hypercorticism and adrenal suppression [see Warnings and Precautions (5.8)]
- Paradoxical bronchospasm [see Warnings and Precautions (5.10)]
- Hypersensitivity reactions including anaphylaxis [see Contraindications (4) and Warnings and Precautions (5.11)]
- Cardiovascular effects [see Warnings and Precautions (5.12)]
- Reduction in bone mineral density [see Warnings and Precautions (5.13)]
- Worsening of narrow-angle glaucoma and cataracts [see Warnings and Precautions (5.14)]
- Worsening of urinary retention [see Warnings and Precautions (5.15)]

6.1 Clinical Trials Experience

Because clinical trials are conducted under widely varying conditions, adverse reaction rates observed in the clinical trials of a drug cannot be directly compared with rates in the clinical trials of another drug and may not reflect the rates observed in practice.

The safety of BREZTRI AEROSPHERE is based on the safety data from one 52-week exacerbation trial (Trial 1) and one 24-week lung function trial with a 28-week safety extension study, resulting in up to 52 weeks of treatment (Trial 2). In Trials 1 and 2, a total of 2783 subjects have received at least 1 dose of BREZTRI AEROSPHERE 320 mcg/18 mcg/9.6 mcg [see Clinical Studies (14)].

In Trials 1 and 2, subjects received one of the following treatments: BREZTRI AEROSPHERE 320 mcg/18 mcg/9.6 mcg, glycopyrrolate and formoterol fumarate [GFF MDI 18 mcg/9.6 mcg], or budesonide and formoterol fumarate [BFF MDI 320 mcg/9.6 mcg]. Each treatment was administered twice daily.

In Trial 1, a 52-week, randomized, double-blind clinical trial, a total of 2144 subjects with COPD received at least 1 dose of BREZTRI AEROSPHERE 320 mcg/18 mcg/9.6 mcg (mean age: 64.7 years, 84.9% Caucasian, 59.7% male across all treatments) [see Clinical Studies (14)].

In Trial 2, a 24-week, randomized, double-blind clinical trial, with a 28-week long-term safety extension resulting in up to 52 weeks of treatment, a total of 639 subjects received at least 1 dose of BREZTRI AEROSPHERE 320 mcg/18 mcg/9.6 mcg (mean age: 65.2 years, 50.1% Caucasian, 71.2% male across all treatments) [see Clinical Studies (14)].

The incidence of adverse reactions from the 52-week trial (Trial 1) is presented in Table 1 for subjects treated with BREZTRI AEROSPHERE 320 mcg/18 mcg/9.6 mcg, GFF MDI 18 mcg/9.6 mcg, or BFF MDI 320 mcg/9.6 mcg.

Table 1: Adverse reactions occurring at an incidence of ≥ 2% of subjects and more common in BREZTRI AEROSPHERE compared to GFF MDI and/or BFF MDI (Trial 1)
Adverse Reaction | BREZTRI AEROSPHERE [BREZTRI AEROSPHERE = budesonide/glycopyrrolate/formoterol fumarate 320 mcg/18 mcg/9.6 mcg; GFF MDI = glycopyrrolate/formoterol fumarate 18 mcg/9.6 mcg; BFF MDI = budesonide/formoterol fumarate 320 mcg/9.6 mcg; all treatments were administered twice daily.]; 320 mcg/18 mcg/9.6 mcg; N=2144 (%) | GFF MDI; 18 mcg/9.6 mcg; N=2125 (%) | BFF MDI; 320 mcg/9.6 mcg; N=2136 (%)
Upper Respiratory Tract Infection | 123 (5.7) | 102 (4.8) | 115 (5.4)
Pneumonia | 98 (4.6) | 61 (2.9) | 107 (5.0)
Back pain | 67 (3.1) | 55 (2.6) | 64 (3.0)
Oral candidiasis | 65 (3.0) | 24 (1.1) | 57 (2.7)
Influenza | 63 (2.9) | 42 (2.0) | 61 (2.9)
Muscle spasms | 60 (2.8) | 19 (0.9) | 53 (2.5)
Urinary tract infection | 58 (2.7) | 60 (2.8) | 41 (1.9)
Cough | 58 (2.7) | 50 (2.4) | 51 (2.4)
Sinusitis | 56 (2.6) | 47 (2.2) | 55 (2.6)
Diarrhea | 44 (2.1) | 37 (1.7) | 38 (1.8)

In 24-week data from Trial 2, adverse reactions that occurred in subjects treated with BREZTRI AEROSPHERE 320 mcg/18 mcg/9.6 mcg (n=639) at an incidence of ≥ 2% included dysphonia (3.1%) and muscle spasms (3.3%).

Additional Adverse Reactions

Other adverse reactions that have been associated with one or more of the individual components of BREZTRI AEROSPHERE include: hyperglycemia, anxiety, insomnia, headache, palpitations, nausea, hypersensitivity, depression, agitation, restlessness, nervousness, tremor, dizziness, angina pectoris, tachycardia, cardiac arrhythmias (e.g., atrial fibrillation, supraventricular tachycardia, and extrasystoles), throat irritation, bronchospasm, dry mouth, bruising, urinary retention, chest pain, sign or symptoms of systemic glucocorticoid steroid effects (e.g., hypofunctional adrenal gland), and abnormal behavior.

7 DRUG INTERACTIONS

No formal drug interaction studies have been performed with BREZTRI AEROSPHERE.

7.1 Inhibitors of Cytochrome P450 3A4

The main route of metabolism of corticosteroids, including budesonide, a component of BREZTRI AEROSPHERE, is via cytochrome P450 isoenzyme 3A4 (CYP3A4). After oral administration of ketoconazole, a strong inhibitor of CYP3A4, the mean plasma concentration of orally administered budesonide increased. Concomitant administration of a CYP3A4 inhibitor may inhibit the metabolism of, and increase the systemic exposure to, budesonide. Caution should be exercised when considering the coadministration of BREZTRI AEROSPHERE with long-term ketoconazole and other known strong CYP3A4 inhibitors (e.g., ritonavir, atazanavir, clarithromycin, indinavir, itraconazole, nefazodone, nelfinavir, saquinavir, telithromycin) [see Warnings and Precautions (5.9)].

7.2 Adrenergic Drugs

If additional adrenergic drugs are to be administered by any route, they should be used with caution because the sympathetic effects of formoterol, a component of BREZTRI AEROSPHERE, may be potentiated [see Warnings and Precautions (5.3)].

7.3 Xanthine Derivatives, Steroids, or Diuretics

Concomitant treatment with xanthine derivatives, steroids, or diuretics may potentiate the hypokalemic effect of beta2-adrenergic agonists such as formoterol, a component of BREZTRI AEROSPHERE.

7.4 Non-Potassium Sparing Diuretics

The hypokalemia and/or ECG changes that may result from the administration of non-potassium sparing diuretics (such as loop or thiazide diuretics) can be acutely worsened by beta2-agonists, especially when the recommended dose of the beta2-agonist is exceeded.

7.5 Monoamine Oxidase Inhibitors, Tricyclic Antidepressants, QTc Prolonging Drugs

BREZTRI AEROSPHERE, as with other beta2-agonists, should be administered with extreme caution to patients being treated with monoamine oxidase inhibitors or tricyclic antidepressants or other drugs known to prolong the QTc interval because the action of adrenergic agonists on the cardiovascular system may be potentiated by these agents. Drugs that are known to prolong the QTc interval may be associated with an increased risk of ventricular arrhythmias.

7.6 Beta-adrenergic Receptor Blocking Agents

Beta-adrenergic receptor antagonists (beta-blockers) and BREZTRI AEROSPHERE may interfere with the effect of each other when administered concurrently. Beta-blockers not only block the therapeutic effects of beta2-agonists, but may produce severe bronchospasm in COPD patients. Therefore, patients with COPD should not normally be treated with beta-blockers. However, under certain circumstances, e.g., as prophylaxis after myocardial infarction, there may be no acceptable alternatives to the use of beta-blockers in patients with COPD. In this setting, cardioselective beta-blockers could be considered, although they should be administered with caution.

7.7 Anticholinergics

There is a potential for an additive interaction with concomitantly used anticholinergic medications. Therefore, avoid coadministration of BREZTRI AEROSPHERE with other anticholinergic-containing drugs as this may lead to an increase in anticholinergic adverse effects [see Warnings and Precautions (5.9, 5.10) and Adverse Reactions (6)].

8 USE IN SPECIFIC POPULATIONS

8.1 Pregnancy

Risk Summary

There are no adequate and well-controlled studies with BREZTRI AEROSPHERE or with two of its individual components, glycopyrrolate or formoterol fumarate, in pregnant women to inform a drug-associated risk; however, studies are available for the other component, budesonide.

In animal reproduction studies, budesonide alone, administered by the subcutaneous route, caused structural abnormalities, was embryocidal, and reduced fetal weights in rats and rabbits at 0.3 and 0.75 times maximum recommended human daily inhaled dose (MRHDID), respectively, but these effects were not seen in rats that received inhaled doses up to 4 times the MRHDID. Studies of pregnant women who received inhaled budesonide alone during pregnancy have not shown increased risk of abnormalities. Experience with oral corticosteroids suggests that rodents are more prone to teratogenic effects from corticosteroid exposure than humans.

Formoterol fumarate alone, administered by the oral route in rats and rabbits, caused structural abnormalities at 1500 and 61,000 times the MRHDID, respectively. Formoterol fumarate was also embryocidal, increased pup loss at birth and during lactation, and decreased pup weight in rats at 110 times the MRHDID. These adverse effects generally occurred at large multiples of the MRHDID when formoterol fumarate was administered by the oral route to achieve high systemic exposures. No structural abnormalities, embryocidal, or developmental effects were seen in rats that received inhalation doses up to 350 times the MRHDID.

Glycopyrrolate alone, administered by the subcutaneous route in rats and rabbits, did not cause structural abnormalities or affect fetal survival at exposures approximately 2700 and 5400 times from MRHDID, respectively. Glycopyrrolate had no effects on the physical, functional, and behavioral development of rat pups with exposures up to 2700 times the MRHDID.

The estimated background risk of major birth defects and miscarriage for the indicated population is unknown. In the U.S. general population, the estimated background risk of major birth defects and miscarriage in clinically recognized pregnancies is 2-4% and 15-20%, respectively.

Clinical Considerations

Labor or Delivery: There are no well-controlled human trials that have investigated the effects of BREZTRI AEROSPHERE on preterm labor or labor at term. Because of the potential for beta-agonist interference with uterine contractility, use of BREZTRI AEROSPHERE during labor should be restricted to those patients in whom the benefits clearly outweigh the risks.

Data

Human Data

Studies of pregnant women have not shown that inhaled budesonide increases the risk of abnormalities when administered during pregnancy. The results from a large population-based prospective cohort epidemiological study reviewing data from three Swedish registries covering approximately 99% of the pregnancies from 1995-1997 (i.e., Swedish Medical Birth Registry; Registry of Congenital Malformations; Child Cardiology Registry) indicate no increased risk for congenital malformations from the use of inhaled budesonide during early pregnancy. Congenital malformations were studied in 2014 infants born to mothers reporting the use of inhaled budesonide for asthma in early pregnancy (usually 10-12 weeks after the last menstrual period), the period when most major organ malformations occur. The rate of recorded congenital malformations was similar compared to the general population rate (3.8% vs. 3.5%, respectively). In addition, after exposure to inhaled budesonide, the number of infants born with orofacial clefts was similar to the expected number in the normal population (4 children vs. 3.3, respectively).

These same data were utilized in a second study bringing the total to 2,534 infants whose mothers were exposed to inhaled budesonide. In this study, the rate of congenital malformations among infants whose mothers were exposed to inhaled budesonide during early pregnancy was not different from the rate for all newborn babies during the same period (3.6%).

Animal Data

Budesonide

In a fertility and reproduction study male rats were subcutaneously dosed for 9 weeks and females for 2 weeks prior to pairing and throughout the mating period. Females were dosed up until weaning of their offspring. Budesonide caused a decrease in prenatal viability and viability of the offspring at birth and during lactation, along with a decrease in maternal body weight gain, at a dose 0.3 times the MRHDID (on a mcg/m^2 basis at maternal subcutaneous doses of 20 mcg/kg/day and above). No such effects were noted at a dose 0.08 times the MRHDID (on a mcg/m2 basis at a maternal subcutaneous dose of 5 mcg/kg/day).

In an embryo-fetal development study in pregnant rabbits dosed during the period of organogenesis from gestation days 6 to 18, budesonide produced fetal loss, decreased fetal weight, and skeletal abnormalities at a dose 0.75 times the MRHDID (on a mcg/m^2 basis at a maternal subcutaneous dose of 25 mcg/kg/day). In an embryo-fetal development study in pregnant rats dosed during the period of organogenesis from gestation days 6-15, budesonide produced similar adverse fetal effects at doses approximately 8 times the MRHDID (on a mcg/m^2 basis at a maternal subcutaneous dose of 500 mcg/kg/day). In another embryo-fetal development study in pregnant rats, no structural abnormalities or embryocidal effects were seen at doses up to 4 times the MRHDID (on a mcg/m^2 basis at maternal inhalation doses up to 250 mcg/kg/day).

In a peri-and post-natal development study, rats dosed from gestation day 15 to postpartum day 21, budesonide had no effects on delivery, but did affect growth and development of offspring. Offspring survival was reduced, and surviving offspring had decreased mean body weights at birth and during lactation at doses 0.3 times the MRHDID and higher (on a mcg/m^2 basis at maternal subcutaneous doses of 20 mcg/kg/day and higher). These findings occurred in the presence of maternal toxicity.

Formoterol Fumarate

In a fertility and reproduction study, male rats were orally dosed for at least 9 weeks and females for 2 weeks prior to pairing and throughout the mating period. Females were either dosed up to gestation day 19 or up until weaning of their offspring. Males were dosed up to 25 weeks. Umbilical hernia was observed in rat fetuses at oral doses 1500 times the MRHDID (on a mcg/m^2 basis at maternal oral doses of 3000 mcg/kg/day and higher). Brachygnathia was observed in rat fetuses at a dose 8000 times the MRHDID (on a mcg/m^2 basis at a maternal oral dose of 15,000 mcg/kg/day). Pregnancy was prolonged at a dose 8000 times the MRHDID (on a mcg/m^2 basis at a maternal oral dose of 15,000 mcg/kg/day). Fetal and pup deaths occurred at doses approximately 1500 times the MRHDID and higher (on a mcg/m^2 basis at oral doses of 3000 mcg/kg/day and higher) during gestation.

In an embryo-fetal development study in pregnant rats dosed during the period of organogenesis from gestation days 6 to 15, no structural abnormalities, embryocidal effects, or developmental effects were seen at doses up to 350 times the MRHDID (on a mcg/m2 basis with maternal inhalation doses up to 690 mcg/kg/day).

In an embryo-fetal development study in pregnant rabbits dosed during the period of organogenesis from gestation days 6 to 18, subcapsular cysts on the liver were observed in the fetuses at a dose 61,000 times the MRHDID (on a mcg/m^2 basis with a maternal oral dose of 60,000 mcg/kg/day). No teratogenic effects were observed at doses up to 3500 times the MRHDID (on a mcg/m^2 basis at maternal oral doses up to 3500 mcg/kg/day).

In a pre- and post-natal development study, pregnant female rats received formoterol at oral doses of 0, 210, 840, and 3400 mcg/kg/day from gestation day 6 (completion of implantation) through the lactation period. Pup survival was decreased from birth to postpartum day 26 at doses 110 times the MRHDID and higher (on a mcg/m^2 basis at maternal oral doses of 210 mcg/kg/day and higher), although there was no evidence of a dose-response relationship. There were no treatment-related effects on the physical, functional, and behavioral development of rat pups.

Glycopyrrolate

In an embryo-fetal development study in pregnant rats dosed during the period of organogenesis from gestation days 6 to 17, glycopyrrolate produced no structural abnormalities or effects on fetal survival; however, slight reductions of fetal body weight in the presence of maternal toxicity at the highest tested dose that was 2700 times the MRHDID (on a mcg/m^2 basis at a maternal subcutaneous dose of 10,000 mcg/kg/day). Fetal body weights were unaffected with doses up to 270 times the MRHDID (on a mcg/m^2 basis with maternal subcutaneous doses up to 1000 mcg/kg/day). Maternal toxicity was observed with doses 270 times the MRHDID and higher (on a mcg/m^2 basis with maternal subcutaneous doses of 1000 mcg/kg/day and higher).

In an embryo-fetal development study in pregnant rabbits dosed during the period of organogenesis from gestation days 6 to 18, glycopyrrolate produced no structural abnormalities or effects on fetal survival; however, slight reductions of fetal body weight in the presence of maternal toxicity at the highest tested dose that was 5400 times the MRHDID (on a mcg/m^2 basis at a maternal subcutaneous dose of 10,000 mcg/kg/day). Fetal body weights were unaffected with doses up to 540 times the MRHDID (on a mcg/m^2 basis with maternal subcutaneous doses up to 1000 mcg/kg/day). Maternal toxicity was observed with doses 540 times the MRHDID and higher (on a mcg/m^2 basis with maternal subcutaneous doses of 1000 mcg/kg/day and higher).

In a pre- and post-natal development study, pregnant female rats received glycopyrrolate at doses of 100, 1000, and 10,000 mcg/kg/day from gestation day 6 through the lactation period. Pup body weight gain was slightly reduced from birth through the lactation period at a dose 2700 times the MRHDID (on a mcg/m^2 basis with a maternal subcutaneous dose of 10,000 mcg/kg/day); however, pup body weight gain was unaffected after weaning. There were no treatment-related effects on the physical, functional, and behavioral development of pups with doses up to 2700 times the MRHDID (on a mcg/m^2 basis with maternal subcutaneous doses up to 10,000 mcg/kg/day). Maternal toxicity was observed from gestation days 6 to 18 with doses 270 times the MRHDID and higher (on a mcg/m^2 basis with maternal subcutaneous doses of 1000 mcg/kg/day and higher).

8.2 Lactation

Risk Summary

There are no available data on the effects of BREZTRI AEROSPHERE, budesonide, glycopyrrolate, or formoterol fumarate on the breastfed child or on milk production. Budesonide, like other ICS, is present in human milk [see Data]. There are no available data on the presence of glycopyrrolate or formoterol fumarate in human milk. Formoterol fumarate and glycopyrrolate have been detected in the plasma of undosed rat pups suckling from exposed dams [see Data]. The developmental and health benefits of breastfeeding should be considered along with the mother's clinical need for BREZTRI AEROSPHERE and any potential adverse effects on the breast-fed child from BREZTRI AEROSPHERE or from the underlying maternal condition.

Data

Human Data

Human data with budesonide delivered via dry powder inhaler indicates that the total daily oral dose of budesonide available in breast milk to the infant is approximately 0.3% to 1% of the dose inhaled by the mother. For BREZTRI AEROSPHERE, the dose of budesonide available to the infant in breast milk, as a percentage of the maternal dose, would be expected to be similar.

There is no available human data for formoterol or glycopyrrolate.

Animal Data

In the fertility and reproduction study in rats, plasma levels of formoterol were measured in pups on post-natal day 15 [see Use in Specific Populations (8.1)]. It was estimated that the maximum plasma concentration that the pups received from the maternal animal, at the highest dose of 15 mg/kg, after nursing was 4.4% (0.24 nmol/L for a litter vs. 5.5 nmol/L for the mother).

In the reproductive/developmental toxicity study in rats, plasma levels of glycopyrrolate were measured in pups on post-natal day 4. The maximum concentration in the pups was 6% of the maternal dose of 10 mg/kg/day (pup plasma concentration of 96 ng/mL at 1 hour after dosing corresponded with 1610 ng/mL in the dam at 0.5 hours after dosing).

8.4 Pediatric Use

BREZTRI AEROSPHERE is not indicated for use in children. The safety and effectiveness of BREZTRI AEROSPHERE in pediatric patients have not been established.

8.5 Geriatric Use

Based on available data, no adjustment of the dosage of BREZTRI AEROSPHERE in geriatric patients is necessary, but greater sensitivity in some older individuals cannot be ruled out.

In Trials 1 and 2, 1100 subjects and 343 subjects, respectively, aged 65 years and older were administered BREZTRI AEROSPHERE 320 mcg/18 mcg/9.6 mcg twice daily. In both trials, no overall differences in safety or effectiveness were observed between these subjects and younger subjects.

8.6 Hepatic Impairment

Formal pharmacokinetic studies using BREZTRI AEROSPHERE have not been conducted in patients with hepatic impairment. However, since budesonide and formoterol fumarate are predominantly cleared by hepatic metabolism, impairment of liver function may lead to accumulation of budesonide and formoterol fumarate in plasma. Therefore, patients with severe hepatic disease should be closely monitored.

8.7 Renal Impairment

Formal pharmacokinetic studies using BREZTRI AEROSPHERE have not been conducted in patients with renal impairment. In patients with severe renal impairment (creatinine clearance of ≤30 mL/min/1.73 m^2) or end-stage renal disease requiring dialysis, BREZTRI AEROSPHERE should only be used if the expected benefit outweighs the potential risk [see Clinical Pharmacology (12.3)].

10 OVERDOSAGE

No cases of overdose have been reported with BREZTRI AEROSPHERE. BREZTRI AEROSPHERE contains budesonide, glycopyrrolate, and formoterol fumarate; therefore, the risks associated with overdosage for the individual components described below apply to BREZTRI AEROSPHERE. Treatment of overdosage consists of discontinuation of BREZTRI AEROSPHERE together with institution of appropriate symptomatic and/or supportive therapy. The judicious use of a cardioselective beta-receptor blocker may be considered, bearing in mind that such medication can produce bronchospasm. Cardiac monitoring is recommended in case of overdosage.

Budesonide

If used at excessive doses for prolonged periods, systemic corticosteroid effects, such as hypercorticism may occur [see Warnings and Precautions (5.8)].

Glycopyrrolate

High doses of glycopyrrolate, a component of BREZTRI AEROSPHERE, may lead to anticholinergic signs and symptoms such as nausea, vomiting, dizziness, lightheadedness, blurred vision, increased intraocular pressure (causing pain, vision disturbances or reddening of the eye), obstipation, or difficulties in voiding.

Formoterol Fumarate

An overdose of formoterol fumarate would likely lead to an exaggeration of effects that are typical for beta2-agonists: seizures, angina, hypertension, hypotension, tachycardia, atrial and ventricular tachyarrhythmias, nervousness, headache, tremor, palpitations, muscle cramps, nausea, dizziness, sleep disturbances, metabolic acidosis, hyperglycemia, hypokalemia. As with all sympathomimetic medications, cardiac arrest, and even death may be associated with overdosage of formoterol fumarate.

11 DESCRIPTION

BREZTRI AEROSPHERE (budesonide, glycopyrrolate and formoterol fumarate) Inhalation Aerosol is a pressurized metered-dose inhaler that delivers a combination of micronized budesonide [an inhaled corticosteroid (ICS)], micronized glycopyrrolate (an anticholinergic), and micronized formoterol fumarate [an inhaled long-acting beta2-adrenergic agonist (a LABA)] for oral inhalation.

Budesonide is a corticosteroid with the following chemical name: (RS)-11β, 16α, 17,21-Tetrahydroxypregna-1,4-diene-3,20-dione cyclic 16,17-acetal with butyraldehyde. Budesonide is a white to off-white, powder which is practically insoluble in water. The molecular formula is C25H34O6 and the molecular weight is 430.54. The structural formula is as follows:

Budesonide contains nine chiral centers and is a mixture of the two epimers (22R and 22S).

Glycopyrrolate is a quaternary ammonium salt with the following chemical name: (RS)-[3-(SR)-Hydroxy-1,1-dimethylpyrrolidinium bromide] α-cyclopentylmandelate. Glycopyrrolate is a powder that is freely soluble in water. The molecular formula is C19H28BrNO3, and the molecular weight is 398.33 g/mol. The structural formula is as follows:

Glycopyrrolate contains two chiral centers and is a racemate of a 1:1 mixture of the R,S and S,R diastereomers. The active moiety, glycopyrronium, is the positively charged ion of glycopyrrolate.

Formoterol fumarate has the chemical name N-[2-Hydroxy-5-[(1RS)-1-hydroxy-2-[[(1RS)-2-(4-methoxyphenyl)-1-methylethyl]-amino] ethyl]phenyl] formamide, (E)-2-butenedioate dihydrate. Formoterol fumarate is a powder that is slightly soluble in water. The molecular formula is (C19H24N2O4)2·C4H4O4·2H2O and the molecular weight is 840.91 g/mol. The structural formula is as follows:

Formoterol fumarate contains two chiral centers and consists of a single enantiomeric pair (a racemate of R,R and S,S).

BREZTRI AEROSPHERE is formulated as a hydrofluoroalkane (HFA 134a) propelled pressurized metered dose inhaler containing 28 or 120 inhalations. The canister has an attached dose indicator and is supplied with a yellow plastic actuator and white mouthpiece with a grey dust cap.

After priming, each actuation of the inhaler meters 170 mcg of budesonide, 9.6 mcg of glycopyrrolate (equivalent to 7.7 mcg of glycopyrronium), and 5.1 mcg of formoterol fumarate (equivalent to 4.4 mcg of formoterol) from the valve which delivers 160 mcg of budesonide, 9.0 mcg of glycopyrrolate (equivalent to 7.2 mcg of glycopyrronium), and 4.8 mcg of formoterol fumarate (equivalent to 4.1 mcg of formoterol) from the actuator. The actual amount of drug delivered to the lung may depend on patient factors, such as the coordination between actuation of the device and inspiration through the delivery system. BREZTRI AEROSPHERE also contains porous particles that form a co-suspension with the drug crystals. The porous particles are comprised of the phospholipid, 1,2-distearoyl-sn-glycero-3-phosphocholine (DSPC), and calcium chloride. Porous particles and HFA 134a are excipients in the formulation.

12 CLINICAL PHARMACOLOGY

12.1 Mechanism of Action

BREZTRI AEROSPHERE

BREZTRI AEROSPHERE contains budesonide, glycopyrrolate, and formoterol fumarate. The mechanism of action described below for the individual components applies to BREZTRI AEROSPHERE. These drugs represent three different classes of medications (a synthetic corticosteroid, an anticholinergic, and a long-acting selective beta2-adrenoceptor agonist) that have different effects on clinical physiology and inflammatory indices of COPD.

Budesonide

Budesonide is an anti-inflammatory corticosteroid that exhibits potent glucocorticoid activity and weak mineralocorticoid activity. In standard in vitro and animal models, budesonide has approximately a 200-fold higher affinity for the glucocorticoid receptor and a 1000-fold higher topical anti-inflammatory potency than cortisol (rat croton oil ear edema assay). As a measure of systemic activity, budesonide is 40 times more potent than cortisol when administered subcutaneously and 25 times more potent when administered orally in the rat thymus involution assay.

In glucocorticoid receptor affinity studies, the 22R epimer of budesonide was two times as active as the 22S epimer. In vitro studies indicated that the two forms of budesonide do not interconvert.

Inflammation is an important component in the pathogenesis of COPD. Corticosteroids have a wide range of inhibitory activities against multiple cell types (e.g., mast cells, eosinophils, neutrophils, macrophages, and lymphocytes) and mediators (e.g., histamine, eicosanoids, leukotrienes, and cytokines) involved in allergic and non-allergic-mediated inflammation. These anti-inflammatory actions of corticosteroids may contribute to their efficacy.

Glycopyrrolate

Glycopyrrolate is a long-acting antimuscarinic agent which is often referred to as an anticholinergic. It has similar affinity to the subtypes of muscarinic receptors M1 to M5. In the airways, it exhibits pharmacological effects through inhibition of the M3 receptor at the smooth muscle leading to bronchodilation. The competitive and reversible nature of antagonism was shown with human and animal origin receptors and isolated organ preparations. In preclinical in vitro as well as in vivo studies, prevention of methylcholine and acetylcholine-induced bronchoconstrictive effects was dose-dependent and lasted more than 12 hours. The clinical relevance of these findings is unknown. The bronchodilation following inhalation of glycopyrrolate is predominantly a site-specific effect.

Formoterol Fumarate

Formoterol fumarate is a long-acting selective beta2-adrenergic agonist (beta2-agonist) with a rapid onset of action. Inhaled formoterol fumarate acts locally in the lung as a bronchodilator. In vitro studies have shown that formoterol has more than 200-fold greater agonist activity at beta2-receptors than at beta1-receptors. The in vitro binding selectivity to beta2- over beta1-adrenoceptors is higher for formoterol than for albuterol (5 times), whereas salmeterol has a higher (3 times) beta2-selectivity ratio than formoterol.

Although beta2-receptors are the predominant adrenergic receptors in bronchial smooth muscle and beta1-receptors are the predominant receptors in the heart, there are also beta2-receptors in the human heart comprising 10% to 50% of the total beta-adrenergic receptors. The precise function of these receptors has not been established, but they raise the possibility that even highly selective beta2-agonists may have cardiac effects.

The pharmacologic effects of beta2-adrenoceptor agonist drugs, including formoterol fumarate, are at least in part attributable to stimulation of intracellular adenyl cyclase, the enzyme that catalyzes the conversion of adenosine triphosphate (ATP) to cyclic-3',5'-adenosine monophosphate (cyclic AMP). Increased cyclic AMP levels cause relaxation of bronchial smooth muscle and inhibition of release of mediators of immediate hypersensitivity from cells, especially from mast cells.

12.2 Pharmacodynamics

Cardiac Electrophysiology

A TQT study was not performed with BREZTRI AEROSPHERE as budesonide is not known to affect the QT interval. However, the potential for QTc interval prolongation with glycopyrrolate/formoterol fumarate was assessed in a double-blind, single-dose, placebo- and positive-controlled crossover trial in 69 healthy subjects. The largest mean (90% upper confidence bound) differences from placebo in baseline-corrected QTcI for 2 inhalations of glycopyrrolate/formoterol fumarate 9/4.8 mcg and glycopyrrolate/formoterol fumarate 72/19.2 mcg, were 3.1 (4.7) ms and 7.6 (9.2) ms, respectively, and excluded the clinically relevant threshold of 10 ms. A dose-dependent increase in heart rate was also observed. The largest mean (90% upper confidence bound) differences from placebo in baseline-corrected heart rate were 3.3 (4.9) beats/min and 7.6 (9.5) beats/min seen within 10 minutes of dosing with 2 inhalations of glycopyrrolate/formoterol fumarate 9/4.8 mcg and glycopyrrolate/formoterol fumarate 72/19.2 mcg, respectively.

Chronic Obstructive Pulmonary Disease

The effects of BREZTRI AEROSPHERE on cardiac rhythm in subjects with COPD was assessed using 24-hour Holter monitoring at Week 16 in a 52-week trial (Trial 1).

The Holter monitoring population in Trial 1 included 180 subjects on BREZTRI AEROSPHERE 320 mcg/18 mcg/9.6 mcg, 160 subjects on glycopyrrolate and formoterol fumarate [GFF MDI 18 mcg/9.6 mcg], and 183 subjects on budesonide/formoterol fumarate [BFF MDI 320 mcg/9.6 mcg]. No clinically meaningful effects on cardiac rhythm were observed.

HPA Axis Effects

Effects of BREZTRI AEROSPHERE on the HPA axis were assessed by measurement of 24-hour serum cortisol at Baseline and Week 24 in subjects with COPD. The geometric mean ratio (Week 24/Baseline) was 0.86 (Co-efficient of variation (CV) =39%) and 0.94 (CV=36.6%) for BREZTRI AEROSPHERE 320 mcg/18mcg/9.6mcg and GFF MDI 18 mcg/9.6 mcg, respectively.

12.3 Pharmacokinetics

Linear pharmacokinetics were demonstrated for budesonide (80 to 320 mcg), glycopyrrolate (18 to 144 mcg), and formoterol fumarate (2.4 to 38.4 mcg). Pharmacokinetic information for glycopyrrolate and formoterol fumarate is for the active moieties, glycopyrronium and formoterol, respectively. The pharmacokinetics of budesonide, glycopyrronium, and formoterol from BREZTRI AEROSPHERE are comparable to the pharmacokinetics of budesonide, glycopyrronium, and formoterol when administered as budesonide/formoterol or glycopyrrolate/formoterol in studies of healthy subjects (single dose) and subjects with COPD (repeated dose).

The pharmacokinetics of the individual components of BREZTRI AEROSPHERE are presented below.

Absorption

Budesonide: Following inhaled administration of BREZTRI AEROSPHERE in subjects with COPD, Cmax occurred within 20 to 40 minutes. Steady state is estimated to be achieved after approximately 1 day of repeated dosing of BREZTRI AEROSPHERE via population pharmacokinetic analysis and the AUC0-12 is approximately 1.3 times higher than after the first dose.

Glycopyrrolate: Following inhaled administration of BREZTRI AEROSPHERE in subjects with COPD, Cmax occurred within 2 to 6 minutes. Steady state is estimated to be achieved after approximately 3 days of repeated dosing of BREZTRI AEROSPHERE via population pharmacokinetic analysis and the AUC0-12 is approximately 1.8 times higher than after the first dose.

Formoterol Fumarate: Following inhaled administration of BREZTRI AEROSPHERE in subjects with COPD, Cmax occurred within 20 to 60 minutes. Steady state is estimated to be achieved after approximately 2 days of repeated dosing with BREZTRI AEROSPHERE via population pharmacokinetic analysis and the AUC0-12 is approximately 1.4 times higher than after the first dose.

Distribution

Budesonide: The estimated budesonide apparent volume of distribution at steady-state in subjects with COPD is approximately 1200 L, via population pharmacokinetic analysis. Over the concentration range of 1-100 nmol/L, mean plasma protein binding of budesonide ranged from 86% to 87%.

Glycopyrrolate: The estimated glycopyrronium apparent volume of distribution at steady-state in subjects with COPD is approximately 5500 L, via population pharmacokinetic analysis. Over the concentration range of 2-500 nmol/L, plasma protein binding of glycopyrronium ranged from 43% to 54%.

Formoterol Fumarate: The estimated formoterol apparent volume of distribution at steady-state in subjects with COPD is approximately 2400 L, via population pharmacokinetic analysis. Over the concentration range of 10-500 nmol/L, plasma protein binding of formoterol ranged from 46% to 58%.

Elimination

Budesonide: Budesonide was excreted in urine and feces in the form of metabolites. Only negligible amounts of unchanged budesonide have been detected in the urine. The effective half-life of budesonide in subjects with COPD derived via population pharmacokinetic analysis was approximately 5 hours.

Glycopyrrolate: After IV administration of a 0.2 mg radiolabeled glycopyrronium, 85% of dose recovered was recovered in urine 48 hours post-dose and some of radioactivity was also recovered in bile. The effective half-life of glycopyrronium in subjects with COPD derived via population pharmacokinetics analysis was approximately 15 hours.

Formoterol Fumarate: The excretion of formoterol was studied in six healthy subjects following simultaneous administration of radiolabeled formoterol via the oral and IV routes. In that study, 62% of the drug related radioactivity of formoterol was excreted in the urine while 24% was eliminated in the feces. The effective half-life of formoterol in subjects with COPD derived via population pharmacokinetics analysis was approximately 10 hours.

Metabolism

Budesonide: In vitro studies with human liver homogenates have shown that budesonide was rapidly and extensively metabolized. Two major metabolites formed via CYP3A4 catalyzed biotransformation have been isolated and identified as 16α-hydroxyprednisolone and 6ß-hydroxybudesonide. The corticosteroid activity of each of these two metabolites was less than 1% of that of the parent compound. No qualitative differences between the in vitro and in vivo metabolic patterns were detected. Negligible metabolic inactivation was observed in human lung and serum preparations.

Glycopyrrolate: Based on information from the published literature, and an in vitro human hepatocyte study, metabolism plays a minor role in the overall elimination of glycopyrronium. CYP2D6 was found to be the predominant enzyme involved in the metabolism of glycopyrronium.

Formoterol Fumarate: The primary metabolism of formoterol is by direct glucuronidation and by O-demethylation followed by conjugation to inactive metabolites. Secondary metabolic pathways include deformylation and sulfate conjugation. CYP2D6 and CYP2C have been identified as being primarily responsible for O-demethylation.

Specific Populations

Population pharmacokinetic analysis showed no evidence of a clinically significant effect of age, sex, race/ethnicity, or body weight on the pharmacokinetics of budesonide, glycopyrronium, or formoterol.

Patients with Hepatic Impairment:

Dedicated studies of BREZTRI AEROSPHERE evaluating effect of hepatic impairment on the pharmacokinetics of budesonide, glycopyrronium, and formoterol were not conducted.

Reduced liver function may affect the elimination of corticosteroids. Budesonide pharmacokinetics was affected by compromised liver function as evidenced by a doubled systemic availability after oral ingestion. The intravenous budesonide pharmacokinetics were, however, similar in cirrhotic patients and in healthy subjects.

As budesonide and formoterol are primarily eliminated via hepatic metabolism, an increased exposure can be expected in patients with severe hepatic impairment.

Patients with Renal Impairment:

Studies with BREZTRI AEROSPHERE evaluating the effect of renal impairment on the pharmacokinetics of budesonide, glycopyrronium, and formoterol were not conducted.

The effect of renal impairment on the exposure to budesonide, glycopyrronium, and formoterol for up to 24 weeks was evaluated in a population pharmacokinetic analysis. Estimated glomerular filtration rate (eGFR) varied from 31-192 mL/min representing a range of moderate to no renal impairment. Simulation of the systemic exposure (AUC0-12) in subjects with COPD with moderate renal impairment (eGFR of 45 mL/min) indicates an approximate 68% increase for glycopyrronium compared to subjects with COPD with normal renal function (eGFR of >90 mL/min). Renal function was found not to significantly affect exposure to budesonide or formoterol after drug clearance adjusted by age or body weight in a population pharmacokinetic analysis.

Drug Interaction Studies

No pharmacokinetic interaction has been observed between budesonide, glycopyrrolate, and formoterol fumarate when administered in combination by the inhaled route. Specific drug interaction studies of BREZTRI AEROSPHERE with other co-administered drugs have not been performed.

Ketoconazole and Itraconazole: Ketoconazole and itraconazole, strong inhibitors of cytochrome P450 (CYP) isoenzyme 3A4 (CYP3A4), the main metabolic enzyme for corticosteroids, increased plasma levels of orally ingested budesonide and orally inhaled budesonide, respectively.

Cimetidine: At recommended doses, cimetidine, a non-specific inhibitor of CYP enzymes, had a slight but clinically insignificant effect on the pharmacokinetics of oral budesonide.

13 NONCLINICAL TOXICOLOGY

13.1 Carcinogenesis, Mutagenesis, Impairment of Fertility

No studies of carcinogenicity, mutagenicity, or impairment of fertility were conducted with BREZTRI AEROSPHERE; however, separate studies of budesonide, glycopyrrolate, and formoterol fumarate are described below.

Budesonide

Long-term studies were conducted in rats and mice using oral administration to evaluate the carcinogenic potential of budesonide.

In a 2-year study in Sprague-Dawley rats, budesonide caused a statistically significant increase in the incidence of gliomas in male rats at an oral dose of 50 mcg/kg (approximately equivalent to the MRHDID on a mcg/m^2 basis). No tumorigenicity was seen in male and female rats at respective oral doses up to 25 and 50 mcg/kg (approximately equivalent to the MRHDID on a mcg/m^2 basis). In two additional 2-year studies in male Fischer and Sprague-Dawley rats, budesonide caused no gliomas at an oral dose of 50 mcg/kg (approximately equivalent to the MRHDID on a mcg/m^2 basis). However, in the male Sprague- Dawley rats, budesonide caused a statistically significant increase in the incidence of hepatocellular tumors at an oral dose of 50 mcg/kg (approximately equivalent to the MRHDID on a mcg/m^2 basis). The concurrent reference corticosteroids (prednisolone and triamcinolone acetonide) in these two studies showed similar findings.

In a 91-week carcinogenicity study in mice, budesonide produced no treatment-related increases in the incidence of tumors at oral doses up to 200 mcg/kg (approximately 2 times the MRHDID on a mcg/m^2 basis).

Budesonide was not mutagenic or clastogenic in the Ames Salmonella/microsome plate test, mouse micronucleus test, mouse lymphoma test, chromosome aberration test in human lymphocytes, sex-linked recessive lethal test in Drosophila melanogaster, and DNA repair analysis in rat hepatocyte culture.

Fertility and reproductive performance were unaffected in rats at subcutaneous doses up to 80 mcg/kg (approximately equal to the MRHDID on a mcg/m^2 basis). However, it caused a decrease in prenatal viability and viability in the pups at birth and during lactation, along with a decrease in maternal body-weight gain, at subcutaneous doses of 20 mcg/kg and above (0.3 times the MRHDID on a mcg/m^2 basis). No such effects were noted at 5 mcg/kg (0.08 times the MRHDID on a mcg/m^2 basis).

Glycopyrrolate

Long-term studies were conducted in mice using inhalation administration and rats using oral administration to evaluate the carcinogenic potential of glycopyrrolate.

In a 24-month inhalation carcinogenicity study in B6C3F1 mice, glycopyrrolate produced no evidence of tumorigenicity when administered to males or females at doses up to 705 and 335 mcg/kg/day, respectively (approximately 95 and 45 times the MRHDID of glycopyrrolate on a mcg/m^2 basis, respectively).

In a 24-month carcinogenicity study in rats, glycopyrrolate produced no evidence of tumorigenicity when administered to males or females by oral gavage at dosages up to 40,000 mcg/kg/day (approximately 11,000 times the MRHDID of glycopyrrolate on a mcg/m^2 basis).

Glycopyrrolate was not mutagenic or clastogenic in the Ames Salmonella/microsome plate test, in vitro mammalian cell micronucleus assay in TK6 cells, or in vivo micronucleus assay in rats.

Fertility and reproductive performance indices were unaffected in male and female rats that received glycopyrrolate by the subcutaneous route at doses up to 10,000 μg/kg/day (approximately 2700 times the MRHDID on a mcg/m^2 basis).

Formoterol Fumarate

Long-term studies were conducted in mice using oral administration and rats using inhalation administration to evaluate the carcinogenic potential of formoterol fumarate.

In a 24-month carcinogenicity study in CD-1 mice, formoterol fumarate at oral doses of 100 mcg/kg and above (approximately 25 times MRHDID on a mcg/m^2 basis) caused a dose-related increase in the incidence of uterine leiomyomas.

In a 24-month carcinogenicity study in Sprague-Dawley rats, an increased incidence of mesovarian leiomyoma and uterine leiomyosarcoma were observed at the inhaled dose of 130 mcg/kg (approximately 65 times the MRHDID on a mcg/m^2 basis). No tumors were seen at 22 mcg/kg (approximately 10 times the MRHDID on a mcg/m^2 basis).

Other beta-agonist drugs have similarly demonstrated increases in leiomyomas of the genital tract in female rodents. The relevance of these findings to human use is unknown.

Formoterol fumarate was not mutagenic or clastogenic in Ames Salmonella/microsome plate test, mouse lymphoma test, chromosome aberration test in human lymphocytes, or rat micronucleus test.

A reduction in fertility and/or reproductive performance was identified in male rats treated with formoterol at an oral dose of 15,000 mcg/kg, (approximately 2600 times the MRHDID on an AUC basis). No such effect was seen at 3,000 mcg/kg (approximately 1500 times the MRHDID on a mcg/m^2 basis). In a separate study with male rats treated with an oral dose of 15,000 mcg/kg (approximately 8000 times the MRHDID on a mcg/m^2 basis), there were findings of testicular tubular atrophy and spermatic debris in the testes and oligospermia in the epididymides. No effect on fertility was detected in female rats at doses up to 15,000 mcg/kg (approximately 1400 times the MRHDID on an AUC basis).

14 CLINICAL STUDIES

The clinical efficacy of BREZTRI AEROSPHERE has been evaluated in two (Trial 1 and 2) randomized, double-blind, multicenter, parallel-group trials in subjects with moderate to very severe COPD who remained symptomatic while receiving 2 or more inhaled maintenance treatments for COPD for at least 6 weeks prior to screening.

Trial 1 (NCT02465567) was conducted over 52 weeks in a total of 8,588 subjects randomized (1:1:1:1) to receive BREZTRI AEROSPHERE (budesonide/glycopyrrolate/formoterol fumarate 320 mcg/18 mcg/9.6 mcg), budesonide, glycopyrrolate and formoterol fumarate [BGF MDI 160 mcg/18 mcg/9.6 mcg] (the BGF MDI 160 mcg/18 mcg/9.6 mcg dosing regimen is not approved), glycopyrrolate and formoterol fumarate [GFF MDI 18 mcg/9.6 mcg], or budesonide and formoterol fumarate [BFF MDI 320 mcg/9.6 mcg], all administered twice daily. GFF MDI and BFF MDI used the same inhaler and excipients as BREZTRI AEROSPHERE.

Trial 1 was conducted in subjects with a history of 1 or more moderate or severe exacerbations in the year prior to screening, post-bronchodilator FEV1/FVC ratio less than 0.7 and the post-bronchodilator FEV1 less than 65% predicted normal value.

The population demographics across all treatments in Trial 1 were: mean age of 65 years, 60% male, 85% Caucasian, and an average smoking history of 48 pack-years, with 41% identified as current smokers. The mean post-bronchodilator percent predicted FEV1 was 43% (range 16% to 73%). At study entry, the most common COPD medications were ICS + long-acting muscarinic antagonist (LAMA) + LABA (39%), ICS + LABA (31%), and LAMA + LABA (14%).

In Trial 1, the primary endpoint was the rate of moderate or severe COPD exacerbations for BREZTRI AEROSPHERE compared with GFF MDI and BFF MDI.

Trial 2 (NCT02497001) was conducted over 24 weeks, in a total of 1,896 subjects randomized (2:2:1:1) to receive BREZTRI AEROSPHERE (budesonide/glycopyrrolate/formoterol fumarate 320 mcg/18 mcg/9.6 mcg), glycopyrrolate and formoterol fumarate [GFF MDI 18 mcg/9.6 mcg], budesonide and formoterol fumarate [BFF MDI 320 mcg/9.6 mcg], or open-label active comparator, all administered twice daily. GFF MDI and BFF MDI used the same inhaler and excipients as BREZTRI AEROSPHERE. Trial 2 was conducted in subjects with a screening post-bronchodilator FEV1/FVC ratio less than 0.7 and post-bronchodilator FEV1 less than 80% predicted normal value. Subjects in Trial 2 were not required to have a history of moderate or severe exacerbations in the year prior to screening.

The population demographics across all treatments in Trial 2 were: mean age of 65 years, 71% male, 50% Caucasian, 45% Asian, and an average smoking history of 52 pack-years, with 40% identified as current smokers. The mean post-bronchodilator percent predicted FEV1 was 50% (range 22% to 84%). At study entry, the most common COPD medications were ICS + LAMA + LABA (27%), ICS + LABA (38%), and LAMA + LABA (20%).

In Trial 2, the primary endpoints were FEV1 area under the curve from 0-4 hours (FEV1 AUC0-4) at Week 24 for BREZTRI AEROSPHERE compared to BFF MDI and change from baseline in morning pre-dose trough FEV1 at Week 24 for BREZTRI AEROSPHERE compared to GFF MDI.

Lung Function

In Trial 1, a subset of subjects were included in a spirometric sub-study with primary endpoints of FEV1 AUC0-4 at Week 24 (mL) and change from baseline in morning pre-dose trough FEV1 at Week 24 (mL). BREZTRI AEROSPHERE demonstrated an increase in on-treatment FEV1 AUC0-4 and trough FEV1 at Week 24 relative to BFF MDI and GFF MDI (Table 2). The effects on lung function (mean change from baseline in on-treatment morning pre-dose trough FEV1) of BREZTRI AEROSPHERE compared with GFF MDI and BFF MDI were observed at all timepoints over the course of the study (Figure 1).

In Trial 2, BREZTRI AEROSPHERE demonstrated an increase in on-treatment FEV1 AUC0-4 at Week 24 relative to BFF MDI and an increase in mean change from baseline in morning pre-dose trough FEV1 at Week 24 compared with GFF MDI (Table 2). The comparison of BREZTRI AEROSPHERE with GFF MDI in mean change from baseline in morning pre-dose trough FEV1 at Week 24 was not statistically significant.

In both trials, there were consistent improvements in lung function in patient subgroups classified by age, sex, degree of airflow limitation (moderate, severe, and very severe), and previous ICS use.

Table 2: Change in FEV1 AUC0-4 and Least Square (LS) Mean Change from Baseline in Morning Pre-dose Trough FEV1 (mL) at Week 24 in Trial 1 (Spirometric Sub-study) and Trial 2 [The analysis excluded spirometry data collected after discontinuation of study treatment.]
Treatment | N | FEV1 AUC0-4 at Week 24 |  | N | Change from baseline in morning pre-dose trough FEV1 at Week 24
Treatment | N | Difference from |  | N | Difference from
 |  | GFF MDI | BFF MDI |  | GFF MDI | BFF MDI
Trial 1 (Sub-study)
BREZTRI AEROSPHERE | 633 | N=588; 53 mL; (29, 77) | N=605; 119 mL; (95, 143) | 634 | N=586; 35 mL; (12, 57) | N=608; 76 mL; (54, 99)
Trial 2
BREZTRI AEROSPHERE | 436 | N=403; 5 mL; (-25, 34) | N=201; 116 mL; (80, 152) | 565 | N=522; 13 mL; (-9, 36) | N=266; 74 mL; (47, 102)

Figure 1: Adjusted Mean Change from Baseline in Trough FEV1 Over Time (Trial 1)1

^1The analysis excluded spirometry data collected after discontinuation of study treatment.

In Trial 2, the median time to onset on Day 1, defined as a 100 mL increase from baseline in FEV1, was within 5 minutes in subjects receiving BREZTRI AEROSPHERE 320 mcg/18 mcg/9.6 mcg. In Trial 1, subjects treated with BREZTRI AEROSPHERE 320 mcg/18 mcg/9.6 mcg on average used less daily rescue medication over 24 weeks compared to subjects treated with GFF MDI 18 mcg/9.6 mcg and BFF MDI 320 mcg/9.6 mcg.

Exacerbations

In Trial 1, the primary endpoint was the rate of on-treatment moderate or severe COPD exacerbations in subjects treated with BREZTRI AEROSPHERE 320 mcg/18 mcg/9.6 mcg compared with GFF MDI and BFF MDI.

Exacerbations were defined as worsening of 2 or more major symptoms (dyspnea, sputum volume, and sputum color) or worsening of any 1 major symptom together with any 1 of the following minor symptoms: cough, wheeze, sore throat, colds (nasal discharge and/or nasal congestion), and fever without other cause for at least 2 consecutive days. Exacerbations were considered to be moderate severity if treatment with systemic corticosteroids and/or antibiotics was required and were considered to be severe if they resulted in hospitalization or death.

In Trial 1, treatment with BREZTRI AEROSPHERE 320 mcg/18 mcg/9.6 mcg demonstrated a reduction in the rate of on-treatment moderate or severe COPD exacerbations over 52 weeks compared with GFF MDI and BFF MDI (see Table 3).

Table 3: Rates of moderate or severe exacerbations over 52 weeks in Trial 1 [On-treatment analyses excluded exacerbation data collected after discontinuation of study treatment.]
Treatment [BREZTRI (BREZTRI AEROSPHERE) = budesonide/glycopyrrolate/formoterol fumarate 320 mcg/18 mcg/9.6 mcg; GFF MDI = glycopyrrolate/formoterol fumarate 18 mcg/9.6 mcg; BFF MDI = budesonide/formoterol fumarate 320 mcg/9.6 mcg] (N) | Mean Annual Rate | Rate Ratio vs. Comparator (95% CI) | % Reduction in Exacerbation Rate (95% CI) | P-Value
BREZTRI AEROSPHERE (N=2137) | 1.08 | N/A | N/A | N/A
GFF MDI (N=2120) | 1.42 | 0.76; (0.69, 0.83) | 24; (17, 31) | p<0.0001
BFF MDI (N=2131) | 1.24 | 0.87; (0.79, 0.95) | 13; (5, 21) | p=0.0027

In Trial 2, treatment with BREZTRI AEROSPHERE 320 mcg/18 mcg/9.6 mcg reduced the annual rate of on-treatment moderate or severe COPD exacerbations compared with GFF MDI 18 mcg/9.6 mcg (rate ratio [95% CI]: 0.48 [0.37, 0.64]), and compared with BFF MDI 320 mcg/9.6 mcg (rate ratio [95% CI]: 0.82 [0.58, 1.17]). The comparison of BREZTRI AEROSPHERE with GFF MDI was not statistically significant due to failure higher in the analysis hierarchy.

Health-Related Quality of Life

In both trials, health-related quality of life was assessed using the St. George’s Respiratory Questionnaire (SGRQ) responder analysis which was defined as an improvement in SGRQ score from baseline of 4 or more.

In Trial 1, the on-treatment percentage of SGRQ responders at Week 24 was greater for subjects treated with BREZTRI AEROSPHERE 320 mcg/18 mcg/9.6 mcg (50%) compared with both GFF MDI 18 mcg/9.6 mcg (43%; odds ratio 1.4; 95% CI: 1.2, 1.5) and BFF MDI 320 mcg/9.6 mcg (45%; odds ratio 1.2; 95% CI: 1.1, 1.4). Similar differences between treatments were observed at Week 52.

In Trial 2, the on-treatment percentage of SGRQ responders at Week 24 was greater for subjects treated with BREZTRI AEROSPHERE 320 mcg/18 mcg/9.6 mcg (50%) compared with both GFF MDI 18 mcg/9.6 mcg (44%; odds ratio 1.3; 95% CI: 1.0, 1.6) and BFF MDI 320 mcg/9.6 mcg (43%; odds ratio 1.3; 95% CI: 1.0, 1.7).

16 HOW SUPPLIED/STORAGE AND HANDLING

BREZTRI AEROSPHERE Inhalation Aerosol:

- 160 mcg budesonide, 9.0 mcg glycopyrrolate, and 4.8 mcg formoterol fumarate per inhalation
- is supplied as a pressurized aluminum canister with an attached dose indicator, a yellow plastic actuator, a white mouthpiece, and a grey plastic dust cap.
- contains 28 or 120 inhalations per canister:

 | Pack size | Net fill weight | NDC
 | 120-inhalation canister | 10.7 grams | 0310-4616-12
 | 28-inhalation canister (institutional pack) | 5.9 grams | 0310-4616-39

- each canister of BREZTRI AEROSPHERE is packaged in a foil laminate pouch with a desiccant sachet and is placed into a carton.
- each carton contains one canister and Patient Information.

The BREZTRI AEROSPHERE canister should only be used with the BREZTRI AEROSPHERE actuator, and the BREZTRI AEROSPHERE actuator should not be used with any other inhalation drug product.

The correct amount of medication in each inhalation cannot be assured after the label number of inhalations from the canister have been used, when the dose indicator display window shows zero in the red zone, even though the canister may not feel completely empty. BREZTRI AEROSPHERE should be discarded when the dose indicator display window shows zero in the red zone or 3 months (for the 120-inhalation canister) or 3 weeks (for the 28-inhalation canister) after removal from the foil pouch, whichever comes first. Never immerse the canister into water to determine the amount remaining in the canister (“float test”).

Store at controlled room temperature 20°C to 25°C (68°F to 77°F); excursions permitted to 15°C to 30°C (59°F to 86°F) [see USP]. Keep in a dry place away from heat and sunlight.

For best results, the canister should be at room temperature before use. Shake well before using. Keep out of reach of children.

CONTENTS UNDER PRESSURE

Do not puncture. Do not use or store near heat or open flames. Exposure to temperatures above 120°F (49°C) may cause bursting. Never throw canister into fire or incinerator. Avoid spraying in eyes.

17 PATIENT COUNSELING INFORMATION

Advise the patient to read the FDA-approved patient labeling (Patient Information and Instructions for Use).

Not for Treatment of Acute Symptoms

Inform patients that BREZTRI AEROSPHERE is not meant to relieve acute symptoms of COPD and extra doses should not be used for that purpose. Advise patients to treat acute symptoms with an inhaled, short-acting beta2-agonist such as albuterol. Provide patients with such medication and instruct them in how it should be used.

Instruct patients to seek medical attention immediately if they experience any of the following:

- Decreasing effectiveness of inhaled, short-acting beta2-agonists
- Need for more inhalations than usual of inhaled, short-acting beta2-agonists
- Significant decrease in lung function as outlined by the health care practitioner

Tell patients they should not stop therapy with BREZTRI AEROSPHERE without physician guidance since symptoms may recur after discontinuation [see Warnings and Precautions (5.2)].

Do Not Use Additional Long-acting Beta2-agonists or Anticholinergics

Instruct patients not to use other LABA or anticholinergic medicines [see Warnings and Precautions (5.3)].

Oropharyngeal Candidiasis

Inform patients that localized infections with Candida albicans occurred in the mouth and pharynx in some patients. If oropharyngeal candidiasis develops, it should be treated with appropriate local or systemic (i.e., oral) antifungal therapy while still continuing therapy with BREZTRI AEROSPHERE, but at times therapy with BREZTRI AEROSPHERE may need to be temporarily interrupted under close medical supervision. Advise patients to rinse the mouth with water without swallowing after inhalation to help reduce the risk of thrush [see Warnings and Precautions (5.4)].

Pneumonia

Patients with COPD have a higher risk of pneumonia; instruct them to contact their healthcare providers if they develop symptoms of pneumonia [see Warnings and Precautions (5.5)].

Immunosuppression and Risk of Infections

Warn patients who are on immunosuppressant doses of corticosteroids to avoid exposure to chickenpox or measles and, if exposed, to consult their physicians without delay. Inform patients of potential worsening of existing tuberculosis, fungal, bacterial, viral, or parasitic infections, or ocular herpes simplex [see Warnings and Precautions (5.6)].

Hypercorticism and Adrenal Suppression

Advise patients that BREZTRI AEROSPHERE may cause systemic corticosteroid effects of hypercorticism and adrenal suppression. Additionally, inform patients that deaths due to adrenal insufficiency have occurred during and after transfer from systemic corticosteroids. Patients should taper slowly from systemic corticosteroids if transferring to BREZTRI AEROSPHERE [see Warnings and Precautions (5.8)].

Paradoxical Bronchospasm

As with other inhaled medicines, BREZTRI AEROSPHERE can cause paradoxical bronchospasm. If paradoxical bronchospasm occurs, instruct patients to discontinue BREZTRI AEROSPHERE and contact their healthcare provider right away [see Warnings and Precautions (5.10)].

Hypersensitivity Reactions, including Anaphylaxis

Advise patients that hypersensitivity reactions (e.g., anaphylaxis, angioedema, rash, urticaria) may occur after administration of BREZTRI AEROSPHERE. Instruct patients to discontinue BREZTRI AEROSPHERE if such reactions occur [see Warnings and Precautions (5.11)].

Reduction in Bone Mineral Density

Advise patients who are at an increased risk for decreased BMD that the use of corticosteroids may pose an additional risk [see Warnings and Precautions (5.13)].

Ocular Effects such as Cataracts or Glaucoma

Inform patients that long-term use of ICS may increase the risk of some eye problems (cataracts or glaucoma); consider regular eye examinations.

Instruct patients to be alert for signs and symptoms of acute narrow-angle glaucoma (e.g., eye pain or discomfort, blurred vision, visual halos or colored images in association with red eyes from conjunctival congestion, and corneal edema). Instruct patients to consult a physician immediately if any of these signs or symptoms develops [see Warnings and Precautions (5.14)].

Worsening of Urinary Retention

Instruct patients to be alert for signs and symptoms of urinary retention (e.g., difficulty passing urine, painful urination). Instruct patients to consult a physician immediately if any of these signs or symptoms develop [see Warnings and Precautions (5.15)].

Risks Associated with Beta-agonist Therapy

Inform patients of adverse effects associated with beta2-agonists, such as palpitations, chest pain, rapid heart rate, tremor, or nervousness. Instruct patients to consult a healthcare practitioner immediately should any of these signs or symptoms develop [see Warnings and Precautions (5.12)].

Manufactured for: AstraZeneca Pharmaceuticals LP, Wilmington, DE 19850

Manufactured by: AstraZeneca Dunkerque Production (AZDP), Dunkerque, France

BREZTRI and AEROSPHERE are trademarks of the AstraZeneca group of companies.

© AstraZeneca 2022

PATIENT INFORMATION

BREZTRI AEROSPHERE® (brez-TREE)

(budesonide, glycopyrrolate, and formoterol fumarate)

inhalation aerosol, for oral inhalation use

What is BREZTRI AEROSPHERE?

BREZTRI AEROSPHERE combines 3 medicines, an inhaled corticosteroid (ICS) medicine (budesonide), an anticholinergic medicine (glycopyrrolate), and a long-acting beta2-adrenergic agonist (LABA) medicine (formoterol fumarate) in 1 inhaler, delivered as a propelled spray.

- ICS medicines such as budesonide help to decrease inflammation in the lungs. Inflammation in the lungs can lead to breathing problems.
- Anticholinergic medicines, such as glycopyrrolate and LABA medicines, such as formoterol fumarate help the muscles around the airways in your lungs stay relaxed to prevent symptoms, such as wheezing, cough, chest tightness, and shortness of breath. These symptoms can happen when the muscles around the airways tighten. This makes it hard to breathe.
- BREZTRI AEROSPHERE is a prescription medicine used long term to treat people with chronic obstructive pulmonary disease (COPD). COPD is a chronic lung disease that includes chronic bronchitis, emphysema, or both.
- BREZTRI AEROSPHERE is used as 2 inhalations, 2 times each day (2 puffs in the morning and 2 puffs in the evening) to improve symptoms of COPD for better breathing and to reduce the number of flare-ups (the worsening of your COPD symptoms for several days).
- BREZTRI AEROSPHERE is not for the treatment of asthma. It is not known if BREZTRI AEROSPHERE is safe and effective in people with asthma. BREZTRI AEROSPHERE contains formoterol fumarate. LABA medicines such as formoterol fumarate when used alone increase the risk of hospitalizations and death from asthma problems. BREZTRI AEROSPHERE contains an ICS, an anticholinergic, and a LABA. When an ICS and LABA are used together, there is not a significant risk in hospitalizations and deaths from asthma problems.
- BREZTRI AEROSPHERE is not to be used to relieve sudden breathing problems and will not replace a rescue inhaler. Always have a rescue inhaler (an inhaled, short-acting bronchodilator) with you to treat sudden breathing problems. If you do not have a rescue inhaler, contact your healthcare provider to have one prescribed for you.
- BREZTRI AEROSPHERE should not be used in children. It is not known if BREZTRI AEROSPHERE is safe and effective in children.

Do not use BREZTRI AEROSPHERE if you are allergic to budesonide, glycopyrrolate, formoterol, or any of the ingredients in BREZTRI AEROSPHERE. See “What are the ingredients in BREZTRI AEROSPHERE?” at the end of this Patient Information leaflet below for a complete list of ingredients in BREZTRI AEROSPHERE.

Before using BREZTRI AEROSPHERE, tell your healthcare provider about all of your medical conditions, including if you:

- have heart problems.
- have high blood pressure.
- have seizures.
- have thyroid problems.
- have diabetes.
- have liver problems.
- have kidney problems.
- have weak bones (osteoporosis).
- have an immune system problem.
- have eye problems such as glaucoma or cataracts. BREZTRI AEROSPHERE may make your glaucoma worse.
- have prostate or bladder problems, or problems passing urine. BREZTRI AEROSPHERE may make these problems worse.
- have any type of viral, bacterial, parasitic, or fungal infection.
- are exposed to chickenpox or measles.
- are pregnant or plan to become pregnant. It is not known if BREZTRI AEROSPHERE may harm your unborn baby.
- are breastfeeding. It is not known if the medicines in BREZTRI AEROSPHERE pass into your breast milk and if they can harm your baby. You and your healthcare provider should decide if you will take BREZTRI AEROSPHERE while breastfeeding.

Tell your healthcare provider about all the medicines you take, including prescription and over-the-counter medicines, vitamins, and herbal supplements. BREZTRI AEROSPHERE and certain other medicines may interact with each other. This may cause serious side effects.

Especially tell your healthcare provider if you take:

- anticholinergics (including tiotropium, ipratropium, aclidinium, and umeclidinium)
- other LABAs (including salmeterol, formoterol fumarate, arformoterol tartrate, vilanterol, olodaterol, and indacaterol)
- atropine
- antifungal or anti-HIV medicines

Know the medicines you take. Keep a list of them to show your healthcare provider and pharmacist each time you get a new medicine.

How should I use BREZTRI AEROSPHERE?

Read the step-by-step instructions for using BREZTRI AEROSPHERE in the Instructions for Use provided with this Patient Information leaflet.

- Before using BREZTRI AEROSPHERE, make sure your healthcare provider has taught you how to use the inhaler and you understand how to use it correctly.
- Use BREZTRI AEROSPHERE exactly as your healthcare provider tells you to use it. Do not use BREZTRI AEROSPHERE more often than prescribed.
- Use 2 inhalations of BREZTRI AEROSPHERE, 2 times each day (2 puffs in the morning and 2 puffs in the evening).
- Do not take more than 2 inhalations of BREZTRI AEROSPHERE 2 times each day.
- If a dose (2 puffs) of BREZTRI AEROSPHERE is missed, it should be taken as soon as possible and the next dose should be taken at the usual time. Do not take more than one dose to make up for a forgotten dose.
- Rinse your mouth with water and spit the water out after each dose (2 puffs) of BREZTRI AEROSPHERE. Do not swallow the water. This will help to reduce the chance of getting a fungus infection (thrush) in the mouth and throat.
- If you take too much BREZTRI AEROSPHERE, call your healthcare provider or go to the nearest hospital emergency room right away if you have any unusual symptoms, such as worsening shortness of breath, chest pain, increased heart rate, or shakiness.
- Do not spray BREZTRI AEROSPHERE in your eyes. If BREZTRI AEROSPHERE gets in your eyes, rinse them well with water. If redness continues, call your healthcare provider.
- Do not use other medicines that contain a LABA or an anticholinergic for any reason. Ask your healthcare provider or pharmacist if any of your other medicines are LABA or anticholinergic containing medicines.
- Do not change or stop any medicines used to control or treat your breathing problems. Your healthcare provider will change your medicines as needed.
- BREZTRI AEROSPHERE does not relieve sudden breathing problems and you should not take extra doses of BREZTRI AEROSPHERE to relieve sudden symptoms. Always have a rescue inhaler with you to treat sudden symptoms. If you do not have a rescue inhaler, call your healthcare provider to have one prescribed for you.
- Call your healthcare provider or get emergency medical care right away if:
  ∘ your breathing problems get worse.
  ∘ you need to use your rescue inhaler more often than usual.
  ∘ your rescue inhaler does not work as well to relieve your symptoms.

What are the possible side effects of BREZTRI AEROSPHERE?

BREZTRI AEROSPHERE can cause serious side effects, including:

- fungal infection in your mouth or throat (thrush). Rinse your mouth with water without swallowing after using BREZTRI AEROSPHERE to help reduce your chance of getting thrush.
- pneumonia. People with COPD have a higher chance of getting pneumonia. BREZTRI AEROSPHERE may increase your chance of getting pneumonia. Call your healthcare provider if you notice any of the following symptoms:

∘ increase in mucus (sputum) production
∘ change in mucus color
∘ fever

∘ chills
∘ increased cough
∘ increased breathing problems

- weakened immune system and increased chance of getting infections (immunosuppression).
- reduced adrenal function (adrenal insufficiency). Adrenal insufficiency is a condition where the adrenal glands do not make enough steroid hormones. This can happen when you stop taking oral corticosteroid medicines (such as prednisone) and start taking a medicine containing an ICS (such as BREZTRI AEROSPHERE). During this transition period, when your body is under stress from fever, trauma (such as a car accident), infection, surgery, or worse COPD symptoms, adrenal insufficiency can get worse and may cause death.
- Symptoms of adrenal insufficiency include:

∘ feeling tired
∘ lack of energy
∘ weakness

∘ nausea and vomiting
∘ low blood pressure (hypotension)

- sudden breathing problems immediately after inhaling your medicine. If you have sudden breathing problems immediately after inhaling your medicine, stop taking BREZTRI AEROSPHERE and call your healthcare provider right away.
- serious allergic reactions. Call your healthcare provider or get emergency medical care if you get any of the following symptoms of a serious allergic reaction:

∘ rash
∘ hives

∘ swelling of your face, mouth, and tongue
∘ breathing problems

- effects on your heart.

∘ increased blood pressure
∘ a fast or irregular heartbeat

∘ chest pain

- effects on your nervous system.

∘ tremor

∘ nervousness

- bone thinning or weakness (osteoporosis).
- new or worsened eye problems including acute narrow-angle glaucoma and cataracts. Acute narrow-angle glaucoma can cause permanent loss of vision if not treated. Symptoms of acute narrow-angle glaucoma may include:

∘ eye pain or discomfort
∘ nausea or vomiting
∘ blurred vision

∘ seeing halos or bright colors around lights
∘ red eyes

If you have these symptoms, call your healthcare provider right away before taking another dose.
2. urinary retention. People who take BREZTRI AEROSPHERE may develop new or worsening urinary retention. Symptoms of urinary retention may include:

∘ difficulty urinating
∘ urinating frequently

∘ painful urination
∘ urination in a weak stream or drips

If you have these symptoms of urinary retention, stop taking BREZTRI AEROSPHERE and call your healthcare provider right away before taking another dose.
2. changes in laboratory blood values, including high levels of blood sugar (hyperglycemia) and low levels of potassium (hypokalemia). Low levels of potassium may cause symptoms of muscle spasm, muscle weakness, or abnormal heart rhythm.

Common side effects of BREZTRI AEROSPHERE include

  ∘ upper respiratory tract infection
  ∘ pneumonia
  ∘ back pain
  ∘ thrush in your mouth and throat. Rinse your mouth with water without swallowing after use to help prevent this.
  ∘ joint pain
  ∘ flu
  ∘ headache
  ∘ high blood sugar levels
  ∘ muscle spasms

∘ cough
∘ inflammation of the sinuses
∘ diarrhea
∘ hoarseness
∘ painful and frequent urination (signs of a urinary tract infection)
∘ nausea
∘ difficulty sleeping
∘ feeling anxious
∘ awareness of your heart beating (palpitations)

Tell your healthcare provider about any side effect that bothers you or that does not go away.

These are not all the possible side effects of BREZTRI AEROSPHERE. Ask your healthcare provider or pharmacist for more information.

Call your doctor for medical advice about side effects. You may report side effects to FDA at 1-800-FDA-1088. You may also report side effects to AstraZeneca at 1-800-236-9933.

How should I store BREZTRI AEROSPHERE?

- Store BREZTRI AEROSPHERE at room temperature between 68ºF to 77ºF (20ºC to 25ºC). Keep in a dry place away from heat and sunlight.
- Store BREZTRI AEROSPHERE in the unopened foil pouch and only open when ready for use.
- Do not put a hole in the BREZTRI AEROSPHERE canister.
- Do not use or store BREZTRI AEROSPHERE near heat or a flame. Temperatures above 120ºF (49ºC) may cause the canister to burst.
- Do not throw the BREZTRI AEROSPHERE canister into a fire or an incinerator.
- Throw away BREZTRI AEROSPHERE 3 months after you open the foil pouch (for the 120-inhalation canister), or 3 weeks after you open the foil pouch (for the 28-inhalation canister), or when the puff indicator reaches zero “0”, whichever comes first.
- Keep BREZTRI AEROSPHERE and all medicines out of the reach of children.

General information about the safe and effective use of BREZTRI AEROSPHERE.

Medicines are sometimes prescribed for purposes other than those listed in a Patient Information leaflet. Do not use BREZTRI AEROSPHERE for a condition for which it was not prescribed. Do not give your BREZTRI AEROSPHERE to other people, even if they have the same condition that you have. It may harm them.

You can ask your healthcare provider or pharmacist for information about BREZTRI AEROSPHERE that is written for healthcare professionals.

What are the ingredients in BREZTRI AEROSPHERE?

Active ingredients: micronized budesonide, micronized glycopyrrolate, and micronized formoterol fumarate

Inactive ingredients: hydrofluoroalkane (HFA 134a) and porous particles (comprised of DSPC [1,2-Distearoyl-sn-glycero-3-phosphocholine] and calcium chloride)

BREZTRI AEROSPHERE is a trademark of the AstraZeneca group of companies. © AstraZeneca 2022

Manufactured for: AstraZeneca Pharmaceuticals LP, Wilmington, DE 19850; Manufactured by: AstraZeneca Dunkerque Production (AZDP), Dunkerque, France

For more information, go to www.BREZTRI.com or call 1-800-236-9933.

This Patient Information has been approved by the U.S. Food and Drug Administration. Issued: January 2022

PATIENT INFORMATION

INSTRUCTIONS FOR USE

BREZTRI AEROSPHERE® (brez-TREE)

(budesonide, glycopyrrolate, and formoterol fumarate)

inhalation aerosol, for oral inhalation use

120 inhalation canister

Read this Instructions for Use before you start using BREZTRI AEROSPHERE and each time you get a new

refill. There may be new information. This information does not take the place of talking to your doctor about

your medical condition or treatment. Your BREZTRI AEROSPHERE inhaler may be different from inhalers

you have used before.

Important information

- For oral inhalation use only
- Prime your BREZTRI AEROSPHERE inhaler before using it for the first time.
- Rinse the yellow actuator 1-time eqach week.
- Take 2 puffs of medicine in the morning and 2 puffs of medicine in the evening.
- Rinse mouth with water after the 2 puffs to reduce your chance of getting a fungal infection.

Storing your inhaler

- Store your inhaler at room temperature between 68°F to 77°F (20°C to 25°C)
- Do not store in a humid environment, such as a bathroom
- Keep your inhaler and all medicines out of the reach of children

Parts of your BREZTRI AEROSPHERE inhaler

Reading the puff indicator

BEFORE FIRST USE – Prime your inhaler 4 times before first use

- Before you use your BREZTRI AEROSPHERE inhaler for the first time, prime it so that you will
get the right amount of medicine when you use it.

DAILY USE - Using your BREZTRI AEROSPHERE inhaler

- Dose: 2 puffs in the morning and 2 puffs in the evening.
- Rinse mouth with water after the 2 puffs to reduce your chance of getting a fungal infection.

WEEKLY RINSE – Rinse your actuator 1-time each week

- Rinse the yellow actuator 1-time each week so that the medicine does not build up and block the
spray through the mouthpiece.
- Do not allow the canister to get wet.
- Re-prime after rinsing.

Throwing away your BREZTRI AEROSPHERE inhaler

Throw away your inhaler in household trash when:

- puff indicator shows 0

or

- 3 months after your inhaler has been removed from the foil pouch.

Do not reuse or use the actuator with medicine canisters from other inhalers.

Do not puncture or throw the canister into a fire or incinerator.

Ordering a new BREZTRI AEROSPHERE inhaler

- Order a new BREZTRI AEROSPHERE inhaler when the pointer on the puff indicator is in the

yellow zone.

BREZTRI AEROSPHERE is a trademark of the AstraZeneca group of companies.

© AstraZeneca 2022

Distributed by: AstraZeneca Pharmaceuticals LP, Wilmington, DE 19850

Revised: January 2022

This “Instructions for Use” has been approved by the U.S. Food and Drug Administration.

PATIENT INFORMATION

INSTRUCTIONS FOR USE

BREZTRI AEROSPHERE® (brez-TREE)

(budesonide, glycopyrrolate, and formoterol fumarate)

inhalation aerosol, for oral inhalation use

28 inhalation canister

Read this Instructions for Use before you start using BREZTRI AEROSPHERE and each time you get a new

refill. There may be new information. This information does not take the place of talking to your doctor about

your medical condition or treatment. Your BREZTRI AEROSPHERE inhaler may be different from inhalers you

have used before.

Important information

- For oral inhalation use only
- Prime your BREZTRI AEROSPHERE inhaler before using it for the first time.
- Take 2 puffs of medicine in the morning and 2 puffs of medicine in the evening.
- Rinse mouth with water after the 2 puffs to reduce your chance of getting a fungal infection.

Storing your inhaler

- Store your inhaler at room temperature between 68°F to 77°F (20°C to 25°C)
- Do not store in a humid environment, such as a bathroom
- Keep your inhaler and all medicines out of the reach of children

Parts of your BREZTRI AEROSPHERE inhaler

Reading the puff indicator

The puff indicator will count down by 1 each time you spray a puff of medicine.

Do not try to take a puff of medicine when the pointer is at 0 because you will not receive a full dose.

BEFORE FIRST USE – Prime your inhaler 4 times before first use

- Before you use your inhaler for the first time, prime it so that you will get the right amount of medicine when you use it.

DAILY USE - Using your BREZTRI AEROSPHERE inhaler

- Dose: 2 puffs in the morning and 2 puffs in the evening.
- Rinse mouth with water after the 2 puffs to reduce your chance of getting a fungal infection.

Throwing away your BREZTRI AEROSPHERE inhaler

Throw away your inhaler in household trash when:

- puff indicator shows 0

or

- 3 weeks after your inhaler has been removed from the foil pouch.

Do not reuse or use the actuator with medicine canisters from other inhalers.

Do not puncture or throw the canister into a fire or incinerator.

Ordering a new BREZTRI AEROSPHERE inhaler

- Order a new BREZTRI AEROSPHERE inhaler when the pointer on the puff indicator is in the

yellow zone.

BREZTRI AEROSPHERE is a trademark of the AstraZeneca group of companies.

© AstraZeneca 2022

Distributed by: AstraZeneca Pharmaceuticals LP, Wilmington, DE 19850

Revised: January 2022

This “Instructions for Use” has been approved by the U.S. Food and Drug Administration.

PACKAGE/LABEL PRINCIPAL DISPLAY PANEL

NDC 0310-4616-12

Rx only

BREZTRI

AEROSPHERE®

(budesonide,glycopyrrolate,

and formoterol fumarate)

Inhalation Aerosol

160 mcg/ 9 mcg / 4.8 mcg

per inhalation

For Oral Inhalation Only

Shake inhaler well before using.

120 Inhalations

AstraZeneca

PACKAGE/LABEL PRINCIPAL DISPLAY PANEL

NDC 0310-4616-39

Rx only

BREZTRI

AEROSPHERE®

(budesonide,glycopyrrolate,

and formoterol fumarate)

Inhalation Aerosol

160 mcg/ 9 mcg / 4.8 mcg

per inhalation

For Oral Inhalation Only

Shake inhaler well before using.

120 Inhalations

AstraZeneca